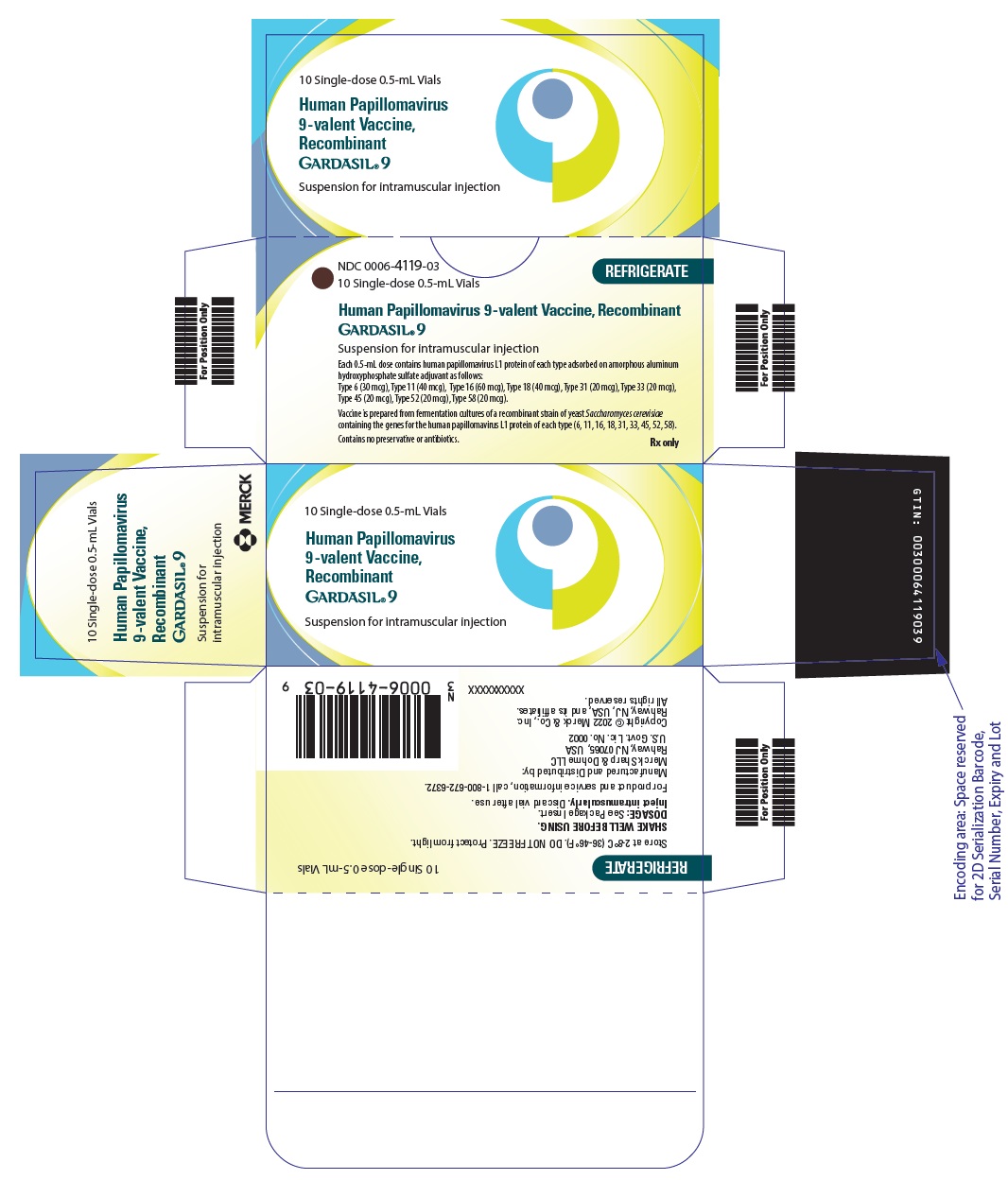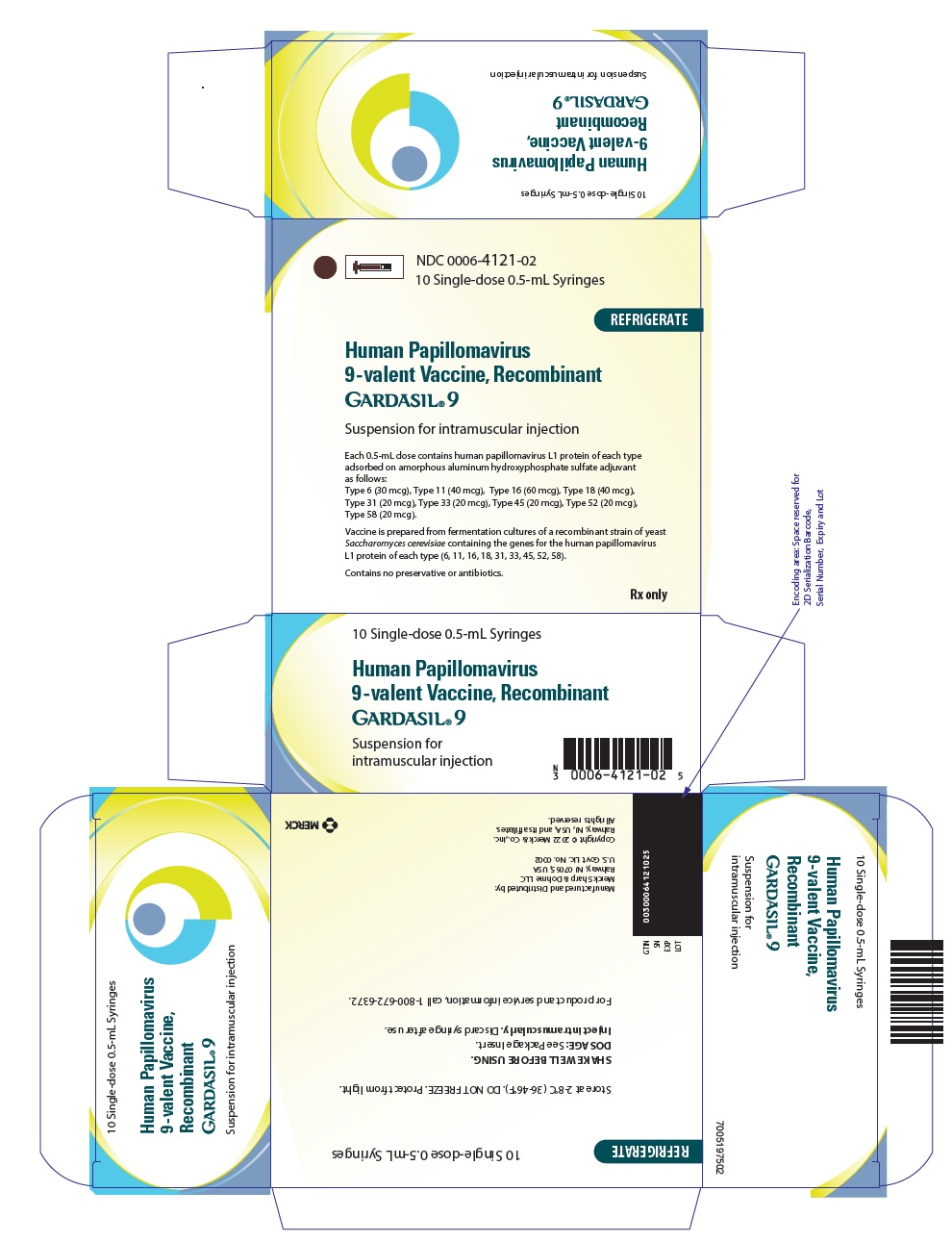 DRUG LABEL: GARDASIL 9
NDC: 0006-4119 | Form: INJECTION, SUSPENSION
Manufacturer: Merck Sharp & Dohme LLC
Category: other | Type: VACCINE LABEL
Date: 20250605

ACTIVE INGREDIENTS: Human Papillomavirus Type 6 L1 Capsid Protein Antigen 30 ug/0.5 mL; Human Papillomavirus Type 11 L1 Capsid Protein Antigen 40 ug/0.5 mL; Human Papillomavirus Type 16 L1 Capsid Protein Antigen 60 ug/0.5 mL; Human Papillomavirus Type 18 L1 Capsid Protein Antigen 40 ug/0.5 mL; Human Papillomavirus Type 31 L1 Capsid Protein Antigen 20 ug/0.5 mL; Human Papillomavirus Type 33 L1 Capsid Protein Antigen 20 ug/0.5 mL; Human Papillomavirus Type 45 L1 Capsid Protein Antigen 20 ug/0.5 mL; Human Papillomavirus Type 52 L1 Capsid Protein Antigen 20 ug/0.5 mL; Human Papillomavirus Type 58 L1 Capsid Protein Antigen 20 ug/0.5 mL
INACTIVE INGREDIENTS: SODIUM CHLORIDE 9.56 mg/0.5 mL; HISTIDINE 0.78 mg/0.5 mL; POLYSORBATE 80 50 ug/0.5 mL; SODIUM BORATE 35 ug/0.5 mL; WATER

HIGHLIGHTS OF PRESCRIBING INFORMATION

These highlights do not include all the information needed to use GARDASIL 9 safely and effectively. See full prescribing information for GARDASIL 9.
GARDASIL®9
(Human Papillomavirus 9-valent Vaccine, Recombinant)
Suspension for intramuscular injection
Initial U.S. Approval: 2014

1 INDICATIONS AND USAGE

GARDASIL 9 is a vaccine indicated in girls and women 9 through 45 years of age for the prevention of the following diseases:

- Cervical, vulvar, vaginal, anal, oropharyngeal and other head and neck cancers caused by Human Papillomavirus (HPV) types 16, 18, 31, 33, 45, 52, and 58. (1.1)
- Genital warts (condyloma acuminata) caused by HPV types 6 and 11. (1.1)

And the following precancerous or dysplastic lesions caused by HPV types 6, 11, 16, 18, 31, 33, 45, 52, and 58:

- Cervical intraepithelial neoplasia (CIN) grade 2/3 and cervical adenocarcinoma in situ (AIS). (1.1)
- Cervical intraepithelial neoplasia (CIN) grade 1. (1.1)
- Vulvar intraepithelial neoplasia (VIN) grade 2 and grade 3. (1.1)
- Vaginal intraepithelial neoplasia (VaIN) grade 2 and grade 3. (1.1)
- Anal intraepithelial neoplasia (AIN) grades 1, 2, and 3. (1.1)

GARDASIL 9 is indicated in boys and men 9 through 45 years of age for the prevention of the following diseases:

- Anal, oropharyngeal and other head and neck cancers caused by HPV types 16, 18, 31, 33, 45, 52, and 58. (1.2)
- Genital warts (condyloma acuminata) caused by HPV types 6 and 11. (1.2)

And the following precancerous or dysplastic lesions caused by HPV types 6, 11, 16, 18, 31, 33, 45, 52, and 58:

- Anal intraepithelial neoplasia (AIN) grades 1, 2, and 3. (1.2)

The oropharyngeal and head and neck cancer indication is approved under accelerated approval based on effectiveness in preventing HPV- related anogenital disease. Continued approval for this indication may be contingent upon verification and description of clinical benefit in a confirmatory trial (1).

Limitations of Use and Effectiveness:

- Vaccination with GARDASIL 9 does not eliminate the necessity for vaccine recipients to undergo screening for cervical, vulvar, vaginal, anal, oropharyngeal and other head and neck cancers as recommended by a health care provider. (1.3, 17)
- GARDASIL 9 has not been demonstrated to provide protection against disease caused by:
  - HPV types not covered by the vaccine
  - HPV types to which a person has previously been exposed through sexual activity. (1.3)
- Not all vulvar, vaginal, anal, oropharyngeal and other head and neck cancers are caused by HPV, and GARDASIL 9 protects only against those vulvar, vaginal, anal, oropharyngeal and other head and neck cancers caused by HPV 16, 18, 31, 33, 45, 52, and 58. (1.3)
- GARDASIL 9 is not a treatment for external genital lesions; cervical, vulvar, vaginal, anal, oropharyngeal and other head and neck cancers; CIN; VIN; VaIN; or AIN. (1.3)
- Vaccination with GARDASIL 9 may not result in protection in all vaccine recipients. (1.3)

2 DOSAGE AND ADMINISTRATION

For intramuscular administration only. (2)

Each dose of GARDASIL 9 is 0.5-mL

Administer GARDASIL 9 as follows: (2.1)

Age | Regimen | Schedule
9 through 14 years | 2-dose | 0, 6 to 12 months [If the second dose is administered earlier than 5 months after the first dose, administer a third dose at least 4 months after the second dose. (14.2 and 14.7)]
9 through 14 years | 3-dose | 0, 2, 6 months
15 through 45 years | 3-dose | 0, 2, 6 months

3 DOSAGE FORMS AND STRENGTHS

- 0.5-mL suspension for injection as a single-dose vial and prefilled syringe. (3, 11)

4 CONTRAINDICATIONS

Hypersensitivity, including severe allergic reactions to yeast (a vaccine component), or after a previous dose of GARDASIL 9 or GARDASIL®. (4, 11)

5 WARNINGS AND PRECAUTIONS

Because vaccinees may develop syncope, sometimes resulting in falling with injury, observation for 15 minutes after administration is recommended. Syncope, sometimes associated with tonic-clonic movements and other seizure-like activity, has been reported following HPV vaccination. When syncope is associated with tonic-clonic movements, the activity is usually transient and typically responds to restoring cerebral perfusion by maintaining a supine or Trendelenburg position. (5.1)

6 ADVERSE REACTIONS

The most common (≥10%) local and systemic adverse reactions reported:

- In girls and women 16 through 26 years of age: injection-site pain (89.9%), injection-site swelling (40.0%), injection-site erythema (34.0%) and headache (14.6%). (6.1)
- In girls 9 through 15 years of age: injection-site pain (89.3%), injection-site swelling (47.8%), injection-site erythema (34.1%) and headache (11.4%). (6.1)
- In women 27 through 45 years of age: injection-site pain (82.8%), injection-site swelling (23.3%), injection-site erythema (16.9%), and headache (13.6%) (6.1)
- In boys and men 16 through 26 years of age: injection-site pain (63.4%), injection-site swelling (20.2%) and injection-site erythema (20.7%). (6.1)
- In boys 9 through 15 years of age: injection-site pain (71.5%), injection-site swelling (26.9%), and injection-site erythema (24.9%). (6.1)

To report SUSPECTED ADVERSE REACTIONS, contact Merck Sharp & Dohme LLC at 1-877-888-4231 or VAERS at 1-800-822-7967 or www.vaers.hhs.gov .

FULL PRESCRIBING INFORMATION

1 INDICATIONS AND USAGE

1.1 Girls and Women

GARDASIL®9 is a vaccine indicated in girls and women 9 through 45 years of age for the prevention of the following diseases:

- Cervical, vulvar, vaginal, anal, oropharyngeal and other head and neck cancers caused by Human Papillomavirus (HPV) types 16, 18, 31, 33, 45, 52, and 58
- Genital warts (condyloma acuminata) caused by HPV types 6 and 11

And the following precancerous or dysplastic lesions caused by HPV types 6, 11, 16, 18, 31, 33, 45, 52, and 58:

- Cervical intraepithelial neoplasia (CIN) grade 2/3 and cervical adenocarcinoma in situ (AIS)
- Cervical intraepithelial neoplasia (CIN) grade 1
- Vulvar intraepithelial neoplasia (VIN) grade 2 and grade 3
- Vaginal intraepithelial neoplasia (VaIN) grade 2 and grade 3
- Anal intraepithelial neoplasia (AIN) grades 1, 2, and 3

1.2 Boys and Men

GARDASIL 9 is indicated in boys and men 9 through 45 years of age for the prevention of the following diseases:

- Anal, oropharyngeal and other head and neck cancers caused by HPV types 16, 18, 31, 33, 45, 52, and 58
- Genital warts (condyloma acuminata) caused by HPV types 6 and 11

And the following precancerous or dysplastic lesions caused by HPV types 6, 11, 16, 18, 31, 33, 45, 52, and 58:

- Anal intraepithelial neoplasia (AIN) grades 1, 2, and 3

The oropharyngeal and head and neck cancer indication is approved under accelerated approval based on effectiveness in preventing HPV-related anogenital disease [see Clinical Studies (14.5)]. Continued approval for this indication may be contingent upon verification and description of clinical benefit in a confirmatory trial.

1.3 Limitations of Use and Effectiveness

- Vaccination with GARDASIL 9 does not eliminate the necessity for vaccine recipients to undergo screening for cervical, vulvar, vaginal, anal, oropharyngeal and other head and neck cancers as recommended by a health care provider.
- GARDASIL 9 has not been demonstrated to provide protection against disease caused by:
  - HPV types not covered by the vaccine [see Description (11)],
  - HPV types to which a person has previously been exposed through sexual activity.
- Not all vulvar, vaginal, anal, oropharyngeal and other head and neck cancers are caused by HPV, and GARDASIL 9 protects only against those vulvar, vaginal, anal, oropharyngeal and other head and neck cancers caused by HPV 16, 18, 31, 33, 45, 52, and 58.
- GARDASIL 9 is not a treatment for external genital lesions; cervical, vulvar, vaginal, anal, oropharyngeal and other head and neck cancers; CIN; VIN; VaIN; or AIN.
- Vaccination with GARDASIL 9 may not result in protection in all vaccine recipients.

2 DOSAGE AND ADMINISTRATION

For intramuscular use only

2.1 Dosage

Each dose of GARDASIL 9 is 0.5-mL.

Administer GARDASIL 9 as follows:

Age | Regimen | Schedule
9 through 14 years | 2-dose | 0, 6 to 12 months [If the second dose is administered earlier than 5 months after the first dose, administer a third dose at least 4 months after the second dose. [See Clinical Studies (14.2 and 14.7).]]
9 through 14 years | 3-dose | 0, 2, 6 months
15 through 45 years | 3-dose | 0, 2, 6 months

2.2 Method of Administration

- Do not dilute or mix GARDASIL 9 with other vaccines.
- Shake well immediately before use to maintain suspension of the vaccine.
- Parenteral drug products should be inspected visually for particulate matter and discoloration prior to administration, whenever solution and container permit. Do not use the product if particulates are present or if it appears discolored. After thorough agitation, GARDASIL 9 is a white cloudy liquid.
- Administer intramuscularly in the deltoid or anterolateral area of the thigh.
- Observe patients for 15 minutes after administration [see Warnings and Precautions (5)].

Single-Dose Vial Use

Withdraw the 0.5-mL dose of vaccine from the single-dose vial using a sterile needle and syringe and use promptly. Discard vial after use.

Prefilled Syringe Use

This package does not contain a needle. Shake well before use. Attach a needle by twisting in a clockwise direction until the needle fits securely on the syringe. Administer the entire dose as per standard protocol. Discard syringe after use.

2.3 Administration of GARDASIL 9 in Individuals Who Have Been Previously Vaccinated with GARDASIL®

Safety and immunogenicity were assessed in individuals who completed a three-dose vaccination series with GARDASIL 9 and had previously completed a three-dose vaccination series with GARDASIL [see Adverse Reactions (6.1) and Clinical Studies (14.6)]. Studies using a mixed regimen of HPV vaccines to assess interchangeability were not performed for GARDASIL 9.

3 DOSAGE FORMS AND STRENGTHS

GARDASIL 9 is a suspension for intramuscular administration available in 0.5-mL single-dose vials and prefilled syringes. [See Description (11)] for the complete listing of ingredients.

4 CONTRAINDICATIONS

Hypersensitivity, including severe allergic reactions to yeast (a vaccine component), or after a previous dose of GARDASIL 9 or GARDASIL [see Description (11)].

5 WARNINGS AND PRECAUTIONS

5.1 Syncope

Because vaccinees may develop syncope, sometimes resulting in falling with injury, observation for 15 minutes after administration is recommended. Syncope, sometimes associated with tonic-clonic movements and other seizure-like activity, has been reported following HPV vaccination. When syncope is associated with tonic-clonic movements, the activity is usually transient and typically responds to restoring cerebral perfusion by maintaining a supine or Trendelenburg position.

5.2 Managing Allergic Reactions

Appropriate medical treatment and supervision must be readily available in case of anaphylactic reactions following the administration of GARDASIL 9.

6 ADVERSE REACTIONS

6.1 Clinical Trials Experience

Because clinical trials are conducted under widely varying conditions, adverse reaction rates observed in the clinical trials of a vaccine cannot be directly compared to rates in the clinical trials of another vaccine and may not reflect the rates observed in practice.

The safety of GARDASIL 9 was evaluated in seven clinical studies that included 15,703 individuals who received at least one dose of GARDASIL 9 and had safety follow-up. Study 1 and Study 3 also included 7,378 individuals who received at least one dose of GARDASIL as a control and had safety follow-up. The vaccines were administered on the day of enrollment and the subsequent doses administered approximately two and six months thereafter. Safety was evaluated using vaccination report card (VRC)-aided surveillance for 14 days after each injection of GARDASIL 9 or GARDASIL.

The individuals who were monitored using VRC-aided surveillance included 9,097 girls and women 16 through 26 years of age, 1,394 boys and men 16 through 26 years of age, and 5,212 girls and boys 9 through 15 years of age (3,436 girls and 1,776 boys) at enrollment who received GARDASIL 9; and 7,078 girls and women 16 through 26 years of age and 300 girls 9 through 15 years of age at enrollment who received GARDASIL. The race distribution of the integrated safety population for GARDASIL 9 was similar between girls and women 16 through 26 years of age (56.8% White; 25.2% Other Races or Multiracial; 14.1% Asian; 3.9% Black), girls and boys 9 through 15 years of age (62.0% White; 19.2% Other Races or Multiracial; 13.5% Asian; 5.4% Black), and boys and men 16 through 26 years of age (62.1% White; 22.6% Other Races or Multiracial; 9.8% Asian; 5.5% Black). The safety of GARDASIL 9 was compared directly to the safety of GARDASIL in two studies (Study 1 and Study 3) for which the overall race distribution of the GARDASIL cohorts (57.0% White; 26.3% Other Races or Multiracial; 13.6% Asian; 3.2% Black) was similar to that of the GARDASIL 9 cohorts.

Safety of GARDASIL 9 in women 27 through 45 years of age was evaluated in a clinical trial comparing 640 women 27 through 45 years of age and 570 girls and women 16 through 26 years of age. The race distribution was similar between women 27 through 45 years of age (97.7% White, 1.6% Asian, 0.3% Other or Multiracial, 0.5% Black) and girls and women 16 through 26 years of age (94.6% White, 3.0% Asian, 1.6% Other or Multiracial, 0.9% Black).

Safety of GARDASIL 9 in men 27 through 45 years of age is inferred from the safety data of GARDASIL 9 in boys and men 9 through 26 years of age and girls and women 9 through 45 years of age and GARDASIL in individuals 9 through 45 years of age.

Injection-Site and Systemic Adverse Reactions

Injection-site reactions (pain, swelling, and erythema) and oral temperature were solicited using VRC-aided surveillance for five days after each injection of GARDASIL 9 during the clinical studies. The rates and severity of these solicited adverse reactions that occurred within five days following each dose of GARDASIL 9 compared with GARDASIL in Study 1 (girls and women 16 through 26 years of age) and Study 3 (girls 9 through 15 years of age) are presented in Table 1. Among subjects who received GARDASIL 9, the rates of injection-site pain were approximately equal across the three reporting time periods. Rates of injection-site swelling and injection-site erythema increased following each successive dose of GARDASIL 9. Recipients of GARDASIL 9 had numerically higher rates of injection-site reactions compared with recipients of GARDASIL.

Table 1: Rates (%) and Severity of Solicited Injection-Site and Systemic Adverse Reactions Occurring within Five Days of Each Vaccination with GARDASIL 9 Compared with GARDASIL (Studies 1 and 3)
 | GARDASIL 9 |  |  |  | GARDASIL
 | Post-dose 1 | Post-dose 2 | Post-dose 3 | Post any dose | Post-dose 1 | Post-dose 2 | Post-dose 3 | Post any dose
Girls and Women 16 through 26 Years of Age
Injection-Site Adverse Reactions | N=7069 | N=6997 | N=6909 | N=7071 | N=7076 | N=6992 | N=6909 | N=7078
Pain, Any | 70.7 | 73.5 | 71.6 | 89.9 | 58.2 | 62.2 | 62.6 | 83.5
Pain, Severe | 0.7 | 1.7 | 2.6 | 4.3 | 0.4 | 1.0 | 1.7 | 2.6
Swelling, Any | 12.5 | 23.3 | 28.3 | 40.0 | 9.3 | 14.6 | 18.7 | 28.8
Swelling, Severe | 0.6 | 1.5 | 2.5 | 3.8 | 0.3 | 0.5 | 1.0 | 1.5
Erythema, Any | 10.6 | 18.0 | 22.6 | 34.0 | 8.1 | 12.9 | 15.6 | 25.6
Erythema, Severe | 0.2 | 0.5 | 1.1 | 1.6 | 0.2 | 0.2 | 0.4 | 0.8
Systemic Adverse Reactions | n=6995 | n=6913 | n=6743 | n=7022 | n=7003 | n=6914 | n=6725 | n=7024
Temperature ≥100°F | 1.7 | 2.6 | 2.7 | 6.0 | 1.7 | 2.4 | 2.5 | 5.9
Temperature ≥102°F | 0.3 | 0.3 | 0.4 | 1.0 | 0.2 | 0.3 | 0.3 | 0.8
Girls 9 through 15 Years of Age
Injection-Site Adverse Reactions | N=300 | N=297 | N=296 | N=299 | N=299 | N=299 | N=294 | N=300
Pain, Any | 71.7 | 71.0 | 74.3 | 89.3 | 66.2 | 66.2 | 69.4 | 88.3
Pain, Severe | 0.7 | 2.0 | 3.0 | 5.7 | 0.7 | 1.3 | 1.7 | 3.3
Swelling, Any | 14.0 | 23.9 | 36.1 | 47.8 | 10.4 | 17.7 | 25.2 | 36.0
Swelling, Severe | 0.3 | 2.4 | 3.7 | 6.0 | 0.7 | 2.7 | 4.1 | 6.3
Erythema, Any | 7.0 | 15.5 | 21.3 | 34.1 | 9.7 | 14.4 | 18.4 | 29.3
Erythema, Severe | 0 | 0.3 | 1.4 | 1.7 | 0 | 0.3 | 1.7 | 2.0
Systemic Adverse Reactions | n=300 | n=294 | n=295 | n=299 | n=299 | n=297 | n=291 | n=300
Temperature ≥100°F | 2.3 | 1.7 | 3.0 | 6.7 | 1.7 | 1.7 | 0 | 3.3
Temperature ≥102°F | 0 | 0.3 | 1.0 | 1.3 | 0.3 | 0.3 | 0 | 0.7
The data for girls and women 16 through 26 years of age are from Study 1 (NCT00543543), and the data for girls 9 through 15 years of age are from Study 3 (NCT01304498).
N=number of subjects vaccinated with safety follow-up
n=number of subjects with temperature data
Pain, Any=mild, moderate, severe or unknown intensity
Pain, Severe=incapacitating with inability to work or do usual activity
Swelling, Any=any size or size unknown
Swelling, Severe=maximum size greater than 2 inches
Erythema, Any=any size or size unknown
Erythema, Severe=maximum size greater than 2 inches

Unsolicited injection-site and systemic adverse reactions (assessed as vaccine-related by the investigator) observed among recipients of either GARDASIL 9 or GARDASIL in Studies 1 and 3 at a frequency of at least 1% are shown in Table 2. Few individuals discontinued study participation due to adverse experiences after receiving either vaccine (GARDASIL 9 = 0.1% vs. GARDASIL <0.1%).

Table 2: Rates (%) of Unsolicited Injection-Site and Systemic Adverse Reactions Occurring among ≥1.0% of Individuals after Any Vaccination with GARDASIL 9 Compared with GARDASIL (Studies 1 and 3)
 | Girls and Women 16 through 26 Years of Age |  | Girls 9 through 15 Years of Age
 | GARDASIL 9 N=7071 | GARDASIL N=7078 | GARDASIL 9 N=299 | GARDASIL N=300
Injection-Site Adverse Reactions (1 to 5 Days Post-Vaccination, Any Dose)
Pruritus | 5.5 | 4.0 | 4.0 | 2.7
Bruising | 1.9 | 1.9 | 0 | 0
Hematoma | 0.9 | 0.6 | 3.7 | 4.7
Mass | 1.3 | 0.6 | 0 | 0
Hemorrhage | 1.0 | 0.7 | 1.0 | 2.0
Induration | 0.8 | 0.2 | 2.0 | 1.0
Warmth | 0.8 | 0.5 | 0.7 | 1.7
Reaction | 0.6 | 0.6 | 0.3 | 1.0
Systemic Adverse Reactions (1 to 15 Days Post-Vaccination, Any Dose)
Headache | 14.6 | 13.7 | 11.4 | 11.3
Pyrexia | 5.0 | 4.3 | 5.0 | 2.7
Nausea | 4.4 | 3.7 | 3.0 | 3.7
Dizziness | 3.0 | 2.8 | 0.7 | 0.7
Fatigue | 2.3 | 2.1 | 0 | 2.7
Diarrhea | 1.2 | 1.0 | 0.3 | 0
Oropharyngeal pain | 1.0 | 0.6 | 2.7 | 0.7
Myalgia | 1.0 | 0.7 | 0.7 | 0.7
Abdominal pain, upper | 0.7 | 0.8 | 1.7 | 1.3
Upper respiratory tract infection | 0.1 | 0.1 | 0.3 | 1.0
The data for girls and women 16 through 26 years of age are from Study 1 (NCT00543543), and the data for girls 9 through 15 years of age are from Study 3 (NCT01304498).
N=number of subjects vaccinated with safety follow-up

In an uncontrolled clinical trial with 639 boys and 1,878 girls 9 through 15 years of age (Study 2), the rates and severity of solicited adverse reactions following each dose of GARDASIL 9 were similar between boys and girls. Rates of solicited and unsolicited injection-site and systemic adverse reactions in boys 9 through 15 years of age were similar to those among girls 9 through 15 years of age. Solicited and unsolicited adverse reactions reported by boys in this study are shown in Table 3.

In another uncontrolled clinical trial with 1,394 boys and men and 1,075 girls and women 16 through 26 years of age (Study 7), the rates of solicited and unsolicited adverse reactions following each dose of GARDASIL 9 among girls and women 16 through 26 years of age were similar to those reported in Study 1. Rates of solicited and unsolicited adverse reactions reported by boys and men 16 through 26 years of age in this study are shown in Table 3.

In an uncontrolled clinical trial with 640 women 27 through 45 years of age and 570 girls and women 16 through 26 years of age (Study 9), the rates of solicited and unsolicited adverse reactions following each dose of GARDASIL 9 among girls and women 16 through 26 years of age were similar to those reported in Study 1. Rates of solicited and unsolicited adverse reactions reported by women 27 through 45 years of age in this study are shown in Table 3.

Table 3: Rates (%) of Solicited and Unsolicited [Unsolicited adverse reactions reported by ≥1% of individuals] Injection-Site and Systemic Adverse Reactions among Boys 9 through 15 Years of Age, among Boys and Men 16 through 26 Years of Age and Women 27 through 45 Years of Age Who Received GARDASIL 9 (Studies 2, 7, and 9)
 | GARDASIL 9
Boys and Men 16 through 26 Years of Age | N=1394
Solicited Adverse Reactions (1-5 Days Post-Vaccination, Any Dose)
Injection-Site Pain, Any | 63.4
Injection-Site Pain, Severe | 0.6
Injection-Site Erythema, Any | 20.7
Injection-Site Erythema, Severe | 0.4
Injection-Site Swelling, Any | 20.2
Injection-Site Swelling, Severe | 1.1
Oral Temperature ≥100.0°F [For oral temperature: number of subjects with temperature data for boys 9 through 15 years of age N=637; for boys and men 16 through 26 years of age N=1,386; for women 27 through 45 years of age N=640] | 4.4
Oral Temperature ≥102°F | 0.6
Unsolicited Injection-Site Adverse Reactions (1-5 Days Post-Vaccination, Any Dose)
Injection-Site Hypersensitivity | 1.0
Injection-Site Pruritus | 1.0
Unsolicited Systemic Adverse Reactions (1-15 Days Post-Vaccination, Any Dose)
Headache | 7.3
Pyrexia | 2.4
Fatigue | 1.4
Dizziness | 1.1
Nausea | 1.0
Boys 9 through 15 Years of Age | N=639
Solicited Adverse Reactions (1-5 Days Post-Vaccination, Any Dose)
Injection-Site Pain, Any | 71.5
Injection-Site Pain, Severe | 0.5
Injection-Site Erythema, Any | 24.9
Injection-Site Erythema, Severe | 1.9
Injection-Site Swelling, Any | 26.9
Injection-Site Swelling, Severe | 5.2
Oral Temperature ≥100.0°F | 10.4
Oral Temperature ≥102°F | 1.4
Unsolicited Injection-Site Adverse Reactions (1-5 Days Post-Vaccination, Any Dose)
Injection-Site Hematoma | 1.3
Injection-Site Induration | 1.1
Unsolicited Systemic Adverse Reactions (1-15 Days Post-Vaccination, Any Dose)
Headache | 9.4
Pyrexia | 8.9
Nausea | 1.3
Women 27 through 45 Years of Age | N=640
Solicited Adverse Reactions (1-5 Days Post-Vaccination, Any Dose)
Injection-Site Pain, Any | 82.8
Injection-Site Pain, Severe | 1.9
Injection-Site Erythema, Any | 16.9
Injection-Site Erythema, Severe | 0.5
Injection-Site Swelling, Any | 23.3
Injection-Site Swelling, Severe | 1.9
Oral Temperature ≥100.0°F | 2.5
Oral Temperature ≥102°F | 0.3
Unsolicited Injection-Site Adverse Reactions (1-5 Days Post-Vaccination, Any Dose)
Injection-Site Pruritus | 1.6
Injection-Site Hematoma | 1.3
Unsolicited Systemic Adverse Reactions (1-15 Days Post-Vaccination, Any Dose)
Headache | 13.6
Fatigue | 3.4
Pyrexia | 1.7
Nausea | 1.7
Oropharyngeal pain | 1.1
The data for GARDASIL 9 boys 9 through 15 years of age are from Study 2 (NCT00943722). The data for boys and men 16 through 26 years of age for GARDASIL 9 are from Study 7 (NCT01651949). The data for women 27 through 45 years of age are from Study 9 (NCT03158220).
N=number of subjects vaccinated with safety follow-up
Pain, Any=mild, moderate, severe or unknown intensity
Pain, Severe=incapacitating with inability to work or do usual activity
Swelling, Any=any size or size unknown
Swelling, Severe=maximum size greater than 2 inches
Erythema, Any=any size or size unknown
Erythema, Severe=maximum size greater than 2 inches

Serious Adverse Events in Clinical Studies

Serious adverse events were collected throughout the entire study period (range one month to 48 months post-last dose) for the seven clinical studies for GARDASIL 9. Out of the 15,705 individuals who were administered GARDASIL 9 and had safety follow-up, 354 reported a serious adverse event; representing 2.3% of the population. As a comparison, of the 7,378 individuals who were administered GARDASIL and had safety follow-up, 185 reported a serious adverse event; representing 2.5% of the population. Four GARDASIL 9 recipients each reported at least one serious adverse event that was determined to be vaccine-related. The vaccine-related serious adverse reactions were pyrexia, allergy to vaccine, asthmatic crisis, and headache.

Deaths in the Entire Study Population

Across the clinical studies, ten deaths occurred (five each in the GARDASIL 9 and GARDASIL groups); none were assessed as vaccine-related. Causes of death in the GARDASIL 9 group included one automobile accident, one suicide, one case of acute lymphocytic leukemia, one case of hypovolemic septic shock, and one unexplained sudden death 678 days following the last dose of GARDASIL 9. Causes of death in the GARDASIL control group included one automobile accident, one airplane crash, one cerebral hemorrhage, one gunshot wound, and one stomach adenocarcinoma.

Systemic Autoimmune Disorders

In all of the clinical trials with GARDASIL 9 subjects were evaluated for new medical conditions potentially indicative of a systemic autoimmune disorder. In total, 2.2% (351/15,703) of GARDASIL 9 recipients and 3.3% (240/7,378) of GARDASIL recipients reported new medical conditions potentially indicative of systemic autoimmune disorders, which were similar to rates reported following GARDASIL, AAHS control, or saline placebo in historical clinical trials.

Clinical Trials Experience for GARDASIL 9 in Individuals Who Have Been Previously Vaccinated with GARDASIL

A clinical study (Study 4) evaluated the safety of GARDASIL 9 in 12- through 26-year-old girls and women who had previously been vaccinated with three doses of GARDASIL. The time interval between the last injection of GARDASIL and the first injection of GARDASIL 9 ranged from approximately 12 to 36 months. Individuals were administered GARDASIL 9 or saline placebo and safety was evaluated using VRC-aided surveillance for 14 days after each injection of GARDASIL 9 or saline placebo in these individuals. The individuals who were monitored included 608 individuals who received GARDASIL 9 and 305 individuals who received saline placebo. Few (0.5%) individuals who received GARDASIL 9 discontinued due to adverse reactions. The vaccine-related adverse experiences that were observed among recipients of GARDASIL 9 at a frequency of at least 1.0% and also at a greater frequency than that observed among saline placebo recipients are shown in Table 4. Overall, the safety profile was similar between individuals vaccinated with GARDASIL 9 who were previously vaccinated with GARDASIL and those who were naïve to HPV vaccination with the exception of numerically higher rates of injection-site swelling and erythema among individuals who were previously vaccinated with GARDASIL (Tables 1 and 4).

Table 4: Rates (%) of Solicited and Unsolicited [Unsolicited adverse reactions reported by ≥1% of individuals] Injection-Site and Systemic Adverse Reactions among Individuals Previously Vaccinated with GARDASIL Who Received GARDASIL 9 or Saline Placebo (Girls and Women 12 through 26 Years of Age) (Study 4)
 | GARDASIL 9 N=608 | Saline Placebo N=305
Solicited Adverse Reactions (1-5 Days Post-Vaccination, Any Dose)
Injection-Site Pain | 90.3 | 38.0
Injection-Site Erythema | 42.3 | 8.5
Injection-Site Swelling | 49.0 | 5.9
Oral Temperature ≥100.0°F [For oral temperature: number of subjects with temperature data GARDASIL 9 N=604; Saline Placebo N=304] | 6.5 | 3.0
Unsolicited Injection-Site Adverse Reactions (1-5 Days Post-Vaccination, Any Dose)
Injection-Site Pruritus | 7.7 | 1.3
Injection-Site Hematoma | 4.8 | 2.3
Injection-Site Reaction | 1.3 | 0.3
Injection-Site Mass | 1.2 | 0.7
Unsolicited Systemic Adverse Reactions (1-15 Days Post-Vaccination, Any Dose)
Headache | 19.6 | 18.0
Pyrexia | 5.1 | 1.6
Nausea | 3.9 | 2.0
Dizziness | 3.0 | 1.6
Abdominal pain, upper | 1.5 | 0.7
Influenza | 1.2 | 1.0
The data for GARDASIL 9 and saline placebo are from Study 4 (NCT01047345).
N=number of subjects vaccinated with safety follow-up

Safety in Concomitant Use with Menactra and Adacel

In Study 5, the safety of GARDASIL 9 when administered concomitantly with Menactra [Meningococcal (Groups A, C, Y and W-135) Polysaccharide Diphtheria Toxoid Conjugate Vaccine] and Adacel [Tetanus Toxoid, Reduced Diphtheria Toxoid and Acellular Pertussis Vaccine Adsorbed (Tdap)] was evaluated in a randomized study of 1,241 boys (n = 620) and girls (n = 621) with a mean age of 12.2 years [see Clinical Studies (14.8)].

Of the 1,237 boys and girls vaccinated, 1,220 had safety follow-up for injection-site adverse reactions. The rates of injection-site adverse reactions were similar between the concomitant group and non-concomitant group (vaccination with GARDASIL 9 separated from vaccination with Menactra and Adacel by 1 month) with the exception of an increased rate of swelling reported at the injection site for GARDASIL 9 in the concomitant group (14.4%) compared to the non-concomitant group (9.4%). The majority of injection-site swelling adverse reactions were reported as being mild to moderate in intensity.

6.2 Postmarketing Experience

The postmarketing adverse experiences were reported voluntarily from a population of uncertain size, therefore, it is not possible to reliably estimate their frequency or to establish a causal relationship to vaccine exposure.

The safety profile of GARDASIL 9 and GARDASIL are similar. The postmarketing safety experience with GARDASIL is relevant to GARDASIL 9 since the vaccines are manufactured similarly and contain the same L1 HPV proteins of four of the same HPV types.

GARDASIL 9

In addition to the adverse reactions reported in the clinical studies, the following adverse experiences have been spontaneously reported during post-approval use of GARDASIL 9:

Gastrointestinal disorders: Vomiting.

Skin and subcutaneous tissue disorders: Urticaria.

General disorders and administration site conditions: Injection-site nodule.

GARDASIL

The following postmarketing adverse experiences have been spontaneously reported for GARDASIL:

Blood and lymphatic system disorders: Autoimmune hemolytic anemia, idiopathic thrombocytopenic purpura, lymphadenopathy.

Respiratory, thoracic and mediastinal disorders: Pulmonary embolus.

Gastrointestinal disorders: Nausea, pancreatitis, vomiting.

General disorders and administration site conditions: Asthenia, chills, death, fatigue, injection-site nodule, malaise.

Immune system disorders: Autoimmune diseases, hypersensitivity reactions including anaphylactic/anaphylactoid reactions, bronchospasm, and urticaria.

Musculoskeletal and connective tissue disorders: Arthralgia, myalgia.

Nervous system disorders: Acute disseminated encephalomyelitis, dizziness, Guillain-Barré syndrome, headache, motor neuron disease, paralysis, seizures, syncope (including syncope associated with tonic-clonic movements and other seizure-like activity) sometimes resulting in falling with injury, transverse myelitis.

Infections and infestations: Cellulitis.

Vascular disorders: Deep venous thrombosis.

7 DRUG INTERACTIONS

7.1 Use with Systemic Immunosuppressive Medications

Immunosuppressive therapies, including irradiation, antimetabolites, alkylating agents, cytotoxic drugs, and corticosteroids (used in greater than physiologic doses), may reduce the immune responses to vaccines [see Use in Specific Populations (8.6)].

8 USE IN SPECIFIC POPULATIONS

8.1 Pregnancy

Risk Summary

All pregnancies have a risk of birth defect, loss, or other adverse outcomes. In the U.S. general population, the estimated background risk of major birth defects and miscarriage in clinically recognized pregnancies is 2% to 4% and 15% to 20%, respectively. There are no adequate and well-controlled studies of GARDASIL 9 in pregnant women. Data from GARDASIL are relevant to GARDASIL 9 because both vaccines are manufactured using the same process and have overlapping compositions. Data were evaluated from pre-licensure studies in which 55 and 62 pregnancies with known outcomes were associated with women inadvertently exposed to GARDASIL and GARDASIL 9, respectively. Pregnancy Exposure Registry data are available from 1640 and 69 prospectively enrolled women with known pregnancy outcomes who were vaccinated with GARDASIL and GARDASIL 9, respectively. Available data do not suggest an increased risk of major birth defects and miscarriage in women who received GARDASIL or GARDASIL 9.

In one developmental toxicity study, 0.5 mL of a vaccine formulation containing between 1 and 1.5 –fold of each of the 9 HPV antigen types was administered to female rats prior to mating and during gestation. In a second study, animals were administered a single human dose (0.5 mL) of GARDASIL 9 prior to mating, during gestation and during lactation. These animal studies revealed no evidence of harm to the fetus due to GARDASIL 9 [see Data].

Data

Human Data

In pre-licensure clinical studies of GARDASIL 9, women underwent pregnancy testing immediately prior to administration of each dose of GARDASIL 9 or control vaccine (GARDASIL). Subjects who were determined to be pregnant were instructed to defer vaccination until the end of their pregnancy. Despite this pregnancy screening regimen, some subjects were vaccinated very early in pregnancy before human chorionic gonadotropin (HCG) was detectable. An analysis was conducted to evaluate pregnancy outcomes for pregnancies with onset within 30 days before or after vaccination with GARDASIL 9 or GARDASIL. Among such pregnancies, there were 62 and 55 with known outcomes (excluding ectopic pregnancies and elective terminations) for GARDASIL 9 and GARDASIL, respectively, including 44 and 48 live births, respectively. The rates of pregnancies that resulted in a miscarriage were 27.4% (17/62) and 12.7% (7/55) in subjects who received GARDASIL 9 or GARDASIL, respectively. The rates of live births with major birth defects were 0% (0/44) and 2.1% (1/48) in subjects who received GARDASIL 9 or GARDASIL, respectively.

A six-year pregnancy registry for GARDASIL 9 enrolled 185 women who were exposed to GARDASIL 9 within one month prior to the last menstrual period (LMP) or at any time during pregnancy, 180 of whom were prospectively followed. After excluding elective terminations (n=1), ectopic pregnancies (n=0) and those lost to follow-up (n=110), there were 69 pregnancies (including one twin pregnancy) with known outcomes. Of the 69 pregnancies, 5 were in women exposed twice during pregnancy. Therefore, there were 74 exposures to GARDASIL 9 during pregnancy: 3 occurred during the 30 days prior to LMP, 34 during the first trimester, 13 during the second trimester, 19 during the third trimester, and 5 in an unknown trimester. Adverse pregnancy outcomes included 3 miscarriages (all in pregnancy exposures during the first trimester) and 3 major birth defects (one each for pregnancy exposure during the 30 days prior to LMP, first trimester, and second trimester). Women who were exposed twice during pregnancy had 0 miscarriages and 0 major birth defects. These data do not suggest an increased risk of major birth defects and miscarriage in women who received GARDASIL 9.

A five-year pregnancy registry enrolled 2,942 women who were exposed to GARDASIL within one month prior to the LMP or at any time during pregnancy, 2,566 of whom were prospectively followed. After excluding elective terminations (n=107), ectopic pregnancies (n=5) and those lost to follow-up (n=814), there were 1,640 pregnancies with known outcomes. Rates of miscarriage and major birth defects were 6.8% of pregnancies (111/1,640) and 2.4% of live born infants (37/1,527), respectively. These rates of assessed outcomes in the prospective population were consistent with estimated background rates.

In two postmarketing studies of GARDASIL (one conducted in the U.S., and the other in Nordic countries), pregnancy outcomes among subjects who received GARDASIL during pregnancy were evaluated retrospectively. Among the 1,740 pregnancies included in the U.S. study database, outcomes were available to assess the rates of major birth defects and miscarriage. Among the 499 pregnancies included in the Nordic study database, outcomes were available to assess the rates of major birth defects. In both studies, rates of assessed outcomes did not suggest an increased risk with the administration of GARDASIL during pregnancy.

Animal Data

Developmental toxicity studies were conducted in female rats. In one study, animals were administered 0.5 mL of a vaccine formulation containing between 1 and 1.5 –fold of each of the 9 HPV antigen types 5 and 2 weeks prior to mating, and on gestation day 6. In a second study, animals were administered a single human dose (0.5 mL) of GARDASIL 9, 5 and 2 weeks prior to mating, on gestation day 6, and on lactation day 7. No adverse effects on pre- and post-weaning development were observed. There were no vaccine-related fetal malformations or variations, or effects on female fertility.

8.2 Lactation

Risk Summary

Available data are not sufficient to assess the effects of GARDASIL 9 on the breastfed infant or on milk production/excretion. The developmental and health benefits of breastfeeding should be considered along with the mother's clinical need for GARDASIL 9 and any potential adverse effects on the breastfed child from GARDASIL 9 or from the underlying maternal condition. For preventive vaccines, the underlying maternal condition is susceptibility to disease prevented by the vaccine.

8.4 Pediatric Use

Safety and effectiveness have not been established in pediatric patients below 9 years of age.

8.5 Geriatric Use

The safety and effectiveness of GARDASIL 9 have not been evaluated in a geriatric population, defined as individuals aged 65 years and over.

8.6 Immunocompromised Individuals

The immunologic response to GARDASIL 9 may be diminished in immunocompromised individuals [see Drug Interactions (7.1)].

11 DESCRIPTION

GARDASIL 9, Human Papillomavirus 9-valent Vaccine, Recombinant, is a non-infectious recombinant 9-valent vaccine prepared from the purified virus-like particles (VLPs) of the major capsid (L1) protein of HPV Types 6, 11, 16, 18, 31, 33, 45, 52, and 58. The L1 proteins are produced by separate fermentations using recombinant Saccharomyces cerevisiae and self-assembled into VLPs. The fermentation process involves growth of S. cerevisiae on chemically-defined fermentation media which include vitamins, amino acids, mineral salts, and carbohydrates. The VLPs are released from the yeast cells by cell disruption and purified by a series of chemical and physical methods. The purified VLPs are adsorbed on preformed aluminum-containing adjuvant (Amorphous Aluminum Hydroxyphosphate Sulfate or AAHS). The 9-valent HPV VLP vaccine is a sterile liquid suspension that is prepared by combining the adsorbed VLPs of each HPV type and additional amounts of the aluminum-containing adjuvant and the final purification buffer.

GARDASIL 9 is a sterile suspension for intramuscular administration. Each 0.5-mL dose contains approximately 30 mcg of HPV Type 6 L1 protein, 40 mcg of HPV Type 11 L1 protein, 60 mcg of HPV Type 16 L1 protein, 40 mcg of HPV Type 18 L1 protein, 20 mcg of HPV Type 31 L1 protein, 20 mcg of HPV Type 33 L1 protein, 20 mcg of HPV Type 45 L1 protein, 20 mcg of HPV Type 52 L1 protein, and 20 mcg of HPV Type 58 L1 protein.

Each 0.5-mL dose of the vaccine also contains approximately 500 mcg of aluminum (provided as AAHS), 9.56 mg of sodium chloride, 0.78 mg of L-histidine, 50 mcg of polysorbate 80, 35 mcg of sodium borate, <7 mcg yeast protein, and water for injection. The product does not contain a preservative or antibiotics.

After thorough agitation, GARDASIL 9 is a white, cloudy liquid.

12 CLINICAL PHARMACOLOGY

12.1 Mechanism of Action

HPV only infects human beings. Animal studies with analogous animal papillomaviruses suggest that the efficacy of L1 VLP vaccines may involve the development of humoral immune responses. Efficacy of GARDASIL 9 against anogenital diseases related to the vaccine HPV types in human beings is thought to be mediated by humoral immune responses induced by the vaccine, although the exact mechanism of protection is unknown.

13 NONCLINICAL TOXICOLOGY

13.1 Carcinogenesis, Mutagenesis, Impairment of Fertility

GARDASIL 9 has not been evaluated for the potential to cause carcinogenicity, genotoxicity or impairment of male fertility.

14 CLINICAL STUDIES

In these studies, seropositive is defined as anti-HPV titer greater than or equal to the pre-specified serostatus cutoff for a given HPV type. Seronegative is defined as anti-HPV titer less than the pre-specified serostatus cutoff for a given HPV type. The serostatus cutoff is the antibody titer level above the assay's lower limit of quantification that reliably distinguishes sera samples classified by clinical likelihood of HPV infection and positive or negative status by previous versions of competitive Luminex Immunoassay (cLIA). The lower limits of quantification and serostatus cutoffs for each of the 9 vaccine HPV types are shown in Table 5 below. PCR positive is defined as DNA detected for a given HPV type. PCR negative is defined as DNA not detected for a given HPV type. The lower limit of detection for the multiplexed HPV PCR assays ranged from 5 to 34 copies per test across the 9 vaccine HPV types.

Table 5: Competitive Luminex Immunoassay (cLIA) Limits of Quantification and Serostatus Cutoffs for GARDASIL 9 HPV Types
HPV Type | cLIA Lower Limit of Quantification (mMU [mMU=milli-Merck Units] /mL) | cLIA Serostatus Cutoff (mMU/mL)
HPV 6 | 16 | 30
HPV 11 | 6 | 16
HPV 16 | 12 | 20
HPV 18 | 8 | 24
HPV 31 | 4 | 10
HPV 33 | 4 | 8
HPV 45 | 3 | 8
HPV 52 | 3 | 8
HPV 58 | 4 | 8

14.1 Efficacy and Effectiveness Data for GARDASIL

Efficacy and effectiveness of GARDASIL are relevant to GARDASIL 9 since the vaccines are manufactured similarly and contain four of the same HPV L1 VLPs.

Individuals 16 through 26 Years of Age

Efficacy of GARDASIL was assessed in five AAHS-controlled, double-blind, randomized clinical trials evaluating 24,596 individuals 16 through 26 years of age (20,541 girls and women and 4,055 boys and men). The results of these trials are shown in Table 6 below.

Table 6: Analysis of Efficacy of GARDASIL in the PPE [The PPE population consisted of individuals who received all three vaccinations within one year of enrollment, did not have major deviations from the study protocol, were naïve (PCR negative and seronegative) to the relevant HPV type(s) (Types 6, 11, 16, and 18) prior to dose 1 and who remained PCR negative to the relevant HPV type(s) through one month post-dose 3 (Month 7).] Population for Vaccine HPV Types
Disease Endpoints | GARDASIL |  | AAHS Control |  | % Efficacy (95% CI)
Disease Endpoints | N | Number of cases | N | Number of cases | % Efficacy (95% CI)
16- through 26-Year-Old Girls and Women [Analyses of the combined trials were prospectively planned and included the use of similar study entry criteria.]
HPV 16- or 18-related CIN 2/3 or AIS | 8493 | 2 | 8464 | 112 | 98.2 (93.5, 99.8)
HPV 16- or 18-related VIN 2/3 | 7772 | 0 | 7744 | 10 | 100.0 (55.5, 100.0)
HPV 16- or 18-related VaIN 2/3 | 7772 | 0 | 7744 | 9 | 100.0 (49.5, 100.0)
HPV 6-, 11-, 16-, or 18-related CIN (CIN 1, CIN 2/3) or AIS | 7864 | 9 | 7865 | 225 | 96.0 (92.3, 98.2)
HPV 6-, 11-, 16-, or 18-related Genital Warts | 7900 | 2 | 7902 | 193 | 99.0 (96.2, 99.9)
HPV 6- and 11-related Genital Warts | 6932 | 2 | 6856 | 189 | 99.0 (96.2, 99.9)
16- through 26-Year-Old Boys and Men
External Genital Lesions HPV 6-, 11-, 16-, or 18-related
External Genital Lesions | 1394 | 3 | 1404 | 32 | 90.6 (70.1, 98.2)
Condyloma | 1394 | 3 | 1404 | 28 | 89.3 (65.3, 97.9)
PIN 1/2/3 | 1394 | 0 | 1404 | 4 | 100.0 (-52.1, 100.0)
HPV 6-, 11-, 16-, or 18-related Endpoint
AIN 1/2/3 | 194 | 5 | 208 | 24 | 77.5 (39.6, 93.3)
AIN 2/3 | 194 | 3 | 208 | 13 | 74.9 (8.8, 95.4)
AIN 1 Condyloma Acuminatum Non-acuminate | 194 194 194 | 4 0 4 | 208 208 208 | 16 6 11 | 73.0 (16.3, 93.4) 100.0 (8.2, 100.0) 60.4 (-33.5, 90.8)
N=Number of individuals with at least one follow-up visit after Month 7
CI=Confidence Interval
Note 1: Point estimates and confidence intervals are adjusted for person-time of follow-up.
Note 2: Table 6 does not include cases due to HPV types not covered by the vaccine.
AAHS = Amorphous Aluminum Hydroxyphosphate Sulfate, CIN = Cervical Intraepithelial Neoplasia, VIN = Vulvar Intraepithelial Neoplasia, VaIN=Vaginal Intraepithelial Neoplasia, PIN=Penile Intraepithelial Neoplasia, AIN=Anal Intraepithelial Neoplasia, AIS=Adenocarcinoma In Situ

In an extension study in females 16 through 26 years of age at enrollment, prophylactic efficacy of GARDASIL through Month 60 against overall cervical and genital disease related to HPV 6, 11, 16, and 18 was 100% (95% CI: 12.3%, 100%) compared to AAHS control.

An extension study in girls and women 16 through 23 years of age used national health care registries in Denmark, Iceland, Norway, and Sweden to monitor endpoint cases of HPV 6-, 11-, 16-, or 18-related CIN (any grade), AIS, cervical cancer, vulvar cancer, or vaginal cancer among 2,650 girls and women 16 through 23 years of age at enrollment who were randomized to vaccination with GARDASIL. An interim analysis of the per-protocol effectiveness population included 1,902 subjects who completed the GARDASIL vaccination series within one year, were naïve to the relevant HPV type through 1 month post-dose 3, had no protocol violations, and had follow-up data available. The median follow-up from the first dose of vaccine was 6.7 years with a range of 2.8 to 8.4 years. At the time of interim analysis, no cases of HPV 6-, 11-, 16-, or 18-related CIN (any grade), AIS, cervical cancer, vulvar cancer, or vaginal cancer were observed over a total of 5,765 person-years at risk.

Girls and Boys 9 through 15 Years of Age

An extension study of 614 girls and 565 boys 9 through 15 years of age at enrollment who were randomized to vaccination with GARDASIL actively followed subjects for endpoint cases of HPV 6-, 11-, 16-, or 18-related persistent infection, CIN (any grade), AIS, VIN, VaIN, cervical cancer, vulvar cancer, vaginal cancer, and external genital lesions from the initiation of sexual activity or age 16 onwards. An interim analysis of the per-protocol effectiveness population included 246 girls and 168 boys who completed the GARDASIL vaccination series within one year, were seronegative to the relevant HPV type at initiation of the vaccination series, and had not initiated sexual activity prior to receiving the third dose of GARDASIL. The median follow-up from the first dose of vaccine was 7.2 years with a range of 0.5 to 8.5 years. At the time of interim analysis, no cases of persistent infection of at least 12 months' duration and no cases of HPV 6-, 11-, 16-, or 18-related CIN (any grade), AIS, VIN, VaIN, cervical cancer, vulvar cancer, vaginal cancer, or external genital lesions were observed over a total 1,105 person-years at risk. There were 4 cases of HPV 6-, 11-, 16-, or 18-related persistent infection of at least 6 months' duration, including 3 cases related to HPV 16 and 1 case related to HPV 6, none of which persisted to 12 months' duration.

Individuals 27 through 45 Years of Age

A clinical trial evaluated efficacy of GARDASIL in 3,253 women 27 through 45 years of age, based on a combined endpoint of HPV 6-, 11-, 16- or 18-related persistent infection, genital warts, vulvar and vaginal dysplastic lesions of any grade, CIN of any grade, AIS, and cervical cancer. These women were randomized 1:1 to receive either GARDASIL or AAHS control. The clinical trial was conducted in two phases: a base study and a long-term study extension. The per-protocol efficacy (PPE) population received all three vaccinations within one year of enrollment, did not have major deviations from the study protocol, were naïve (PCR negative and seronegative) to the relevant HPV type(s) (Types 6, 11, 16 and 18) prior to dose 1 and remained PCR negative to the relevant HPV type(s) through one month post-dose 3 (Month 7).

In the base study (median duration of follow-up of 3.5 years post-dose 3), the efficacy of GARDASIL against the combined incidence of HPV 6-, 11-, 16-, and 18-related persistent infection, genital warts, VIN, VaIN, vulvar cancer, vaginal cancer, cervical dysplasia (any grade CIN), AIS and cervical cancer in the PPE population was 87.7% (95% CI: 75.4%, 94.6%). The efficacy estimate for the combined endpoint was driven primarily by prevention of persistent infection. The efficacy of GARDASIL against the combined incidence of HPV 6-, 11-, 16-, and 18-related genital warts or cervical dysplasia was 95.0% (95% CI: 68.7%, 99.9%) in the PPE population. While no statistically significant efficacy was demonstrated for GARDASIL in the base study for prevention of cervical intraepithelial neoplasia grades 2 and 3 (CIN 2/3), adenocarcinoma in situ (AIS) or cervical cancer related to HPV types 16 and 18, there was 1 case of CIN 2/3 observed in the GARDASIL group and 5 cases in the placebo group. The CIN 2 case in the GARDASIL group tested positive by PCR for HPV 16 and HPV 51.

In the long-term extension of this study, subjects from Colombia (n=600) randomized to the GARDASIL group in the base study were monitored for HPV 6-, 11-, 16-, and 18-related genital warts or cervical dysplasia. The median follow-up post-dose 3 was 8.9 years with a range of 0.1 to 10.1 years over a total of 3,518 person-years. During the long-term extension phase, no cases of HPV 6-, 11-, 16-, or 18-related CIN (any grade) or genital warts were observed in the PPE population.

Effectiveness of GARDASIL in men 27 through 45 years of age is inferred from efficacy data in women 27 through 45 years of age as described above and supported by immunogenicity data from a clinical trial in which 150 men, 27 through 45 years of age, received a 3-dose regimen of GARDASIL (0, 2, 6 months). A cross-study analysis of per-protocol immunogenicity populations compared Month 7 anti-HPV 6, 11, 16, and 18 GMTs of these 27- through 45-year-old men (Study A) to those of 16- through 26-year old boys and men (Study B) in whom efficacy of GARDASIL had been established (see Table 6). GMT ratios (Study A/Study B) for HPV 6, 11, 16, and 18 were 0.82 (95%CI: 0.65, 1.03), 0.79 (95%CI: 0.66, 0.93), 0.91 (95%CI: 0.72, 1.13), and 0.74 (95%CI: 0.59, 0.92), respectively.

14.2 Clinical Trials for GARDASIL 9

Efficacy and/or immunogenicity of the 3-dose regimen of GARDASIL 9 were assessed in seven clinical trials. Study 1 evaluated the efficacy of GARDASIL 9 to prevent HPV-related cervical, vulvar, and vaginal disease using GARDASIL as a comparator.

The analysis of efficacy for GARDASIL 9 was evaluated in the per-protocol efficacy (PPE) population of 16- through 26-year-old girls and women, who received all three vaccinations within one year of enrollment, did not have major deviations from the study protocol, and were naïve to the relevant HPV type(s) by serology and PCR of cervicovaginal specimens prior to dose one and who remained PCR negative for the relevant HPV type(s) through one month post-dose 3 (Month 7). Overall, approximately 52% of subjects were negative to all vaccine HPV types by both PCR and serology at Day 1.

The primary analysis of efficacy against HPV Types 31, 33, 45, 52, and 58 is based on a combined endpoint of Cervical Intraepithelial Neoplasia (CIN) 2, CIN 3, Adenocarcinoma in situ (AIS), invasive cervical carcinoma, Vulvar Intraepithelial Neoplasia (VIN) 2/3, Vaginal Intraepithelial Neoplasia (VaIN) 2/3, vulvar cancer, or vaginal cancer. Other endpoints evaluated include cervical, vulvar and vaginal disease of any grade, persistent infection, cytological abnormalities and invasive procedures. For all endpoints, the efficacy against the HPV Types 31, 33, 45, 52 and 58 in GARDASIL 9 was evaluated compared with GARDASIL. Efficacy of GARDASIL 9 against anal lesions caused by HPV Types 31, 33, 45, 52, and 58 was not assessed due to low incidence. Effectiveness of GARDASIL 9 against anal lesions was inferred from the efficacy of GARDASIL against anal lesions caused by HPV types 6, 11, 16 and 18 in men and antibody responses elicited by GARDASIL 9 against the HPV types covered by the vaccine.

Effectiveness against disease caused by HPV Types 6, 11, 16, and 18 was assessed by comparison of geometric mean titers (GMTs) of type-specific antibodies following vaccination with GARDASIL 9 with those following vaccination with GARDASIL (Study 1 and Study 3). The effectiveness of GARDASIL 9 in girls and boys 9 through 15 years old and in boys and men 16 through 26 years old was inferred based on a comparison of type-specific antibody GMTs to those of 16 through 26-year-old girls and women following vaccination with GARDASIL 9. Immunogenicity analyses were performed in the per-protocol immunogenicity (PPI) population consisting of individuals who received all three vaccinations within pre-defined day ranges, did not have major deviations from the study protocol, met pre-defined day range for serum collection for assessment of antibody response and were naïve [PCR negative (in girls and women 16 through 26 years of age; Studies 1 and 2) and seronegative (Studies 1, 2, 3, 5, 7 and 8)] to the relevant HPV type(s) prior to dose 1 and among 16- through 26-year-old girls and women (Studies 1 and 2) remained PCR negative to the relevant HPV type(s) through Month 7. Pre-defined day ranges for vaccinations were relative to Day 1 (dose 1). For the 3-dose schedule, dose 2 was at 2 months (± 3 weeks) and dose 3 was at 6 months (± 4 weeks). For the 2-dose schedule, dose 2 was at 6 or 12 months (± 4 weeks). Pre-defined day range for serum collection for assessment of antibody response was 21 to 49 days after the last dose.

Study 1 evaluated immunogenicity of GARDASIL 9 and efficacy to prevent infection and disease caused by HPV types 6, 11, 16, 18, 31, 33, 45, 52, and 58 in 16- through 26-year-old girls and women. Study 2 evaluated immunogenicity of GARDASIL 9 in girls and boys 9 through 15 years of age and women 16 through 26 years of age. Study 3 evaluated immunogenicity of GARDASIL 9 compared with GARDASIL in girls 9 through 15 years of age. Study 4 evaluated administration of GARDASIL 9 to girls and women 12 through 26 years of age previously vaccinated with GARDASIL. Study 5 evaluated GARDASIL 9 concomitantly administered with Menactra and Adacel in girls and boys 11 through 15 years of age. Together, these five clinical trials evaluated 12,233 individuals who received GARDASIL 9 (8,048 girls and women 16 through 26 years of age at enrollment with a mean age of 21.8 years; 2,927 girls 9 through 15 years of age at enrollment with a mean age of 11.9 years; and 1,258 boys 9 through 15 years of age at enrollment with a mean age of 11.9 years. Study 7 evaluated immunogenicity of GARDASIL 9 in boys and men, including 1,106 self-identified as heterosexual men (HM) and 313 self-identified as men having sex with men (MSM), 16 through 26 years of age at enrollment (mean ages 20.8 years and 22.2 years, respectively) and 1,101 girls and women 16 through 26 years of age at enrollment (mean age 21.3 years). Study 9 evaluated immunogenicity of GARDASIL 9 in 640 women 27 through 45 years of age and 570 girls and women 16 through 26 years of age (mean ages 35.8 years and 21.6 years, respectively).

The race distribution of the 16- through 26-year-old girls and women in the clinical trials was as follows: 56.8% White; 25.2% Other; 14.1% Asian; and 3.9% Black. The race distribution of the 9- through 15-year-old girls in the clinical trials was as follows: 60.3% White; 19.3% Other; 13.5% Asian; and 7.0% Black. The race distribution of the 9- through 15-year-old boys in the clinical trials was as follows: 46.6% White; 34.3% Other; 13.3% Asian; and 5.9% Black. The race distribution of the 16- through 26-year-old boys and men in the clinical trials was as follows: 62.1% White; 22.6% Other; 9.8% Asian; and 5.5% Black.

In Study 9 the race distribution of 27- through 45-year-old women was as follows: 97.7% White, 1.6% Asian, 0.3% Other or Multiracial, and 0.5% Black. The race distribution of girls and women 16 through 26 years of age in this study was as follows: 94.6% White, 3.0% Asian, 1.6% Other or Multiracial, and 0.9% Black.

One clinical trial (Study 8) assessed the 2-dose regimen of GARDASIL 9. Study 8 evaluated the immunogenicity of 2 doses of GARDASIL 9 in girls and boys 9 through 14 years of age and 3 doses of GARDASIL 9 in girls 9 through 14 years of age and women 16 through 26 years of age; (N=1,518; 753 girls; 451 boys and 314 women). The mean age for the girls and boys 9 through 14 years of age was 11.5 years; the mean age for girls and women 16 through 26 years of age was 21.0 years. In Study 8, the race distribution was as follows: 61.1% White; 16.3% Asian; 13.3% Other; and 8.9% Black.

14.3 Efficacy – HPV Types 31, 33, 45, 52 and 58 in Girls and Women 16 through 26 Years of Age

Studies Supporting the Efficacy of GARDASIL 9 against HPV Types 31, 33, 45, 52, and 58

The efficacy of GARDASIL 9 in 16- through 26-year-old girls and women was assessed in an active comparator-controlled, double-blind, randomized clinical trial (Study 1) that included a total of 14,204 women (GARDASIL 9 = 7,099; GARDASIL = 7,105) who were enrolled and vaccinated without pre-screening for the presence of HPV infection. Subjects were followed up with a median duration of 40 months (range 0 to 64 months) after the last vaccination.

The primary efficacy evaluation was conducted in the PPE population based on a composite clinical endpoint of HPV 31-, 33-, 45-, 52-, and 58-related cervical cancer, vulvar cancer, vaginal cancer, CIN 2/3 or AIS, VIN 2/3, and VaIN 2/3. Efficacy was further evaluated with the clinical endpoints of HPV 31-, 33-, 45-, 52-, and 58-related CIN 1, vulvar and vaginal disease of any grade, and persistent infection. In addition, the study also evaluated the impact of GARDASIL 9 on the rates of HPV 31-, 33-, 45-, 52-, and 58-related abnormal Papanicolaou (Pap) tests, cervical and external genital biopsy, and definitive therapy [including loop electrosurgical excision procedure (LEEP) and conization]. Efficacy for all endpoints was measured starting after the Month 7 visit.

GARDASIL 9 prevented HPV 31-, 33-, 45-, 52-, and 58-related persistent infection and disease and also reduced the incidence of HPV 31-, 33-, 45-, 52-, and 58-related Pap test abnormalities, cervical and external genital biopsy, and definitive therapy (Table 7).

Table 7: Analysis of Efficacy of GARDASIL 9 against HPV Types 31, 33, 45, 52, and 58 in the PPE [The PPE population consisted of individuals who received all three vaccinations within one year of enrollment, did not have major deviations from the study protocol, were naïve (PCR negative and seronegative) to the relevant HPV type(s) (Types 31, 33, 45, 52, and 58) prior to dose 1, and who remained PCR negative to the relevant HPV type(s) through one month post-dose 3 (Month 7); data from Study 1 (NCT00543543).] Population of 16- through 26-Year-old Girls and Women (Study 1)
Disease Endpoint | GARDASIL 9 N [N=Number of individuals randomized to the respective vaccination group who received at least one injection] =7099 |  | GARDASIL N=7105 |  | GARDASIL 9 Efficacy % (95% CI)
Disease Endpoint | n [n=Number of individuals contributing to the analysis] | Number of cases | n | Number of cases | GARDASIL 9 Efficacy % (95% CI)
HPV 31-, 33-, 45-, 52-, 58-related CIN 2/3, AIS, Cervical Cancer, VIN 2/3, VaIN 2/3, Vulvar Cancer, and Vaginal Cancer | 6016 | 1 | 6017 | 30 | 96.7 (80.9, 99.8)
HPV 31-, 33-, 45-, 52-, 58-related CIN 1 | 5948 | 1 | 5943 | 69 | 98.6 (92.4, 99.9)
HPV 31-, 33-, 45-, 52-, 58-related CIN 2/3 or AIS | 5948 | 1 | 5943 | 27 | 96.3 (79.5, 99.8)
HPV 31-, 33-, 45-, 52-, 58-related Vulvar or Vaginal Disease | 6009 | 1 | 6012 | 16 | 93.8 (61.5, 99.7)
HPV 31-, 33-, 45-, 52-, 58-related Persistent Infection ≥6 Months [Persistent infection detected in samples from two or more consecutive visits at least six months apart] | 5939 | 26 | 5953 | 642 | 96.2 (94.4, 97.5)
HPV 31-, 33-, 45-, 52-, 58-related Persistent Infection ≥12 Months [Persistent infection detected in samples from two or more consecutive visits over 12 months or longer] | 5939 | 15 | 5953 | 375 | 96.1 (93.7, 97.9)
HPV 31-, 33-, 45-, 52-, 58-related ASC-US HR-HPV Positive or Worse Pap [Papanicolaou test] Abnormality | 5881 | 35 | 5882 | 462 | 92.6 (89.7, 94.8)
HPV 31-, 33-, 45-, 52-, 58-related Biopsy | 6016 | 7 | 6017 | 222 | 96.9 (93.6, 98.6)
HPV 31-, 33-, 45-, 52-, 58-related Definitive Therapy [Including loop electrosurgical excision procedure (LEEP) and conization] | 6012 | 4 | 6014 | 32 | 87.5 (65.7, 96.0)
CI=Confidence Interval
CIN=Cervical Intraepithelial Neoplasia, VIN=Vulvar Intraepithelial Neoplasia, VaIN=Vaginal Intraepithelial Neoplasia, AIS=Adenocarcinoma In Situ, ASC-US=Atypical squamous cells of undetermined significance
HR=High Risk

14.4 Long term Follow-up of Individuals Vaccinated with GARDASIL 9

In an extension study of individuals in Study 2, 971 girls and 301 boys 9 through 15 years of age at enrollment who received a 3-dose regimen of GARDASIL 9 were actively followed from age 16 onwards for endpoint cases of HPV 6-, 11-, 16-, 18-, 31-, 33-, 45-, 52-, and 58-related persistent infection and disease. For girls, disease endpoints assessed included HPV 6-, 11-, 16-, 18-, 31-, 33-, 45-, 52-, and 58-related CIN (any grade), AIS, VIN, VaIN, external genital warts, cervical cancer, vulvar cancer and vaginal cancer. For boys, the disease endpoints assessed included HPV 6-, 11-, 16-, 18-, 31-, 33-, 45-, 52-, and 58-related PIN, external genital warts, penile cancer, perineal cancer and perianal cancer.

Analysis of the per-protocol population included 872 girls and 262 boys who completed the GARDASIL 9 vaccination series within one year, were seronegative to the relevant HPV type at initiation of the vaccination series and had not initiated sexual activity prior to receiving the third dose of GARDASIL 9. The median follow-up from the last dose of vaccine was 10.0 years with a range of 3.0 to 11.0 years in girls 9 through 15 years of age and 9.9 years with a range of 3.0 to 10.6 years in boys 9 through 15 years of age.

In girls, no cases of HPV 6-, 11-, 16-, 18-, 31-, 33-, 45-, 52-, and 58-related CIN 2/3, AIS, VIN, VaIN, external genital warts, cervical cancer, vulvar cancer or vaginal cancer were observed over a total of 4,576.1 person-years at risk. One case of CIN1 that tested positive for HPV 16, 39 and 59 by PCR was observed. In boys, no cases of HPV 6-, 11-, 16-, 18-, 31-, 33-, 45-, 52-, and 58-related PIN, external genital warts, penile cancer, perineal cancer or perianal cancer were observed over a total of 1,278.6 person-years at risk.

Incidence rates of vaccine HPV types-related persistent infections of at least 6 months duration in girls and boys observed during the study were 52.4 (95% CI: 33.6, 78.0) and 54.6 (95% CI: 21.9, 112.4) cases per 10,000 person-years, respectively, and within the range of incidence rates reported in vaccinated cohorts of similar age based on results from previous efficacy studies of GARDASIL 9, (which were 36.6 and 21.5 per 10,000 person years for HPV 6-, 11-, 16- and 18-related and HPV 31-, 33-, 45-, 52-, and 58-related persistent infections, respectively, in females in Study 1) and GARDASIL (which were 30 and 59 per 10,000 person-years, for HPV 6-, 11-, 16- and 18-related persistent infections in GARDASIL studies in females and males, respectively).

14.5 Effectiveness in Prevention of HPV-Related Oropharyngeal and Other Head and Neck Cancers

The effectiveness of GARDASIL 9 against oropharyngeal and other head and neck cancers caused by HPV types 16, 18, 31, 33, 45, 52 and 58, is based on the effectiveness of GARDASIL and GARDASIL 9 to prevent anogenital disease caused by HPV types covered by the vaccine [see Clinical Studies (14.1, 14.2, 14.3)].

14.6 Immunogenicity of a 3-Dose Regimen

The minimum anti-HPV titer that confers protective efficacy has not been determined.

Type-specific immunoassays (i.e., cLIA) with type-specific standards were used to assess immunogenicity to each vaccine HPV type. These assays measured antibodies against neutralizing epitopes for each HPV type. The scales for these assays are unique to each HPV type; thus, comparisons across types and to other assays are not appropriate. Immunogenicity was measured by (1) the percentage of individuals who were seropositive for antibodies against the relevant vaccine HPV type, and (2) the Geometric Mean Titer (GMT).

Studies Supporting the Effectiveness of GARDASIL 9 against HPV Types 6, 11, 16, and 18

Effectiveness of GARDASIL 9 against persistent infection and disease related to HPV Types 6, 11, 16, or 18 was inferred from non-inferiority comparisons in Study 1 (16- through 26-year-old girls and women) and Study 3 (9- through 15-year-old girls) of GMTs following vaccination with GARDASIL 9 with those following vaccination with GARDASIL. A low number of efficacy endpoint cases related to HPV types 6, 11, 16 and 18 in both vaccination groups precluded a meaningful assessment of efficacy using disease endpoints associated with these HPV types. The primary analyses were conducted in the per-protocol population, which included subjects who received all three vaccinations within one year of enrollment, did not have major deviations from the study protocol, and were HPV-naïve. HPV-naïve individuals were defined as seronegative to the relevant HPV type(s) prior to dose 1 and among female subjects 16 through 26 years of age in Study 1 PCR negative to the relevant HPV type(s) in cervicovaginal specimens prior to dose 1 through Month 7.

Anti-HPV 6, 11, 16 and 18 GMTs at Month 7 for GARDASIL 9 among girls 9 through 15 years of age and young women 16 through 26 years of age were non-inferior to those among the corresponding populations for GARDASIL (Table 8). At least 99.7% of individuals included in the analyses for each HPV type became seropositive by Month 7.

Table 8: Comparison of Immune Responses (Based on cLIA) Between GARDASIL 9 and GARDASIL for HPV Types 6, 11, 16, and 18 in the PPI [The PPI population consisted of individuals who received all three vaccinations within pre-defined day ranges, did not have major deviations from the study protocol, met predefined criteria for the interval between the Month 6 and Month 7 visit, were naïve (PCR negative [among 16- through 26-year old girls and women] and seronegative) to the relevant HPV type(s) (types 6, 11, 16, and 18) prior to dose 1, and among 16- through 26-year-old girls and women remained PCR negative to the relevant HPV type(s) through one month post-dose 3 (Month 7). The data for 16- through 26-year-old girls and women are from Study 1 (NCT00543543), and the data for 9- through 15-year-old girls are from Study 3 (NCT01304498).] Population of 9- through 26-Year-Old Girls and Women (Studies 1 and 3)
Population | GARDASIL 9 |  | GARDASIL |  | GARDASIL 9/ GARDASIL
Population | N [N=Number of individuals randomized to the respective vaccination group who received at least one injection] (n [n=Number of individuals contributing to the analysis]) | GMT mMU [mMU=milli-Merck Units] /mL | N (n) | GMT mMU/mL | GMT Ratio | (95% CI) [Demonstration of non-inferiority required that the lower bound of the 95% CI of the GMT ratio be greater than 0.67]
Anti-HPV 6
9- through 15-year-old girls | 300 (273) | 1679.4 | 300 (261) | 1565.9 | 1.07 | (0.93, 1.23)
16- through 26-year-old girls and women | 6792 (3993) | 893.1 | 6795 (3975) | 875.2 | 1.02 | (0.99, 1.06)
Anti-HPV 11
9- through 15-year-old girls | 300 (273) | 1315.6 | 300 (261) | 1417.3 | 0.93 | (0.80, 1.08)
16- through 26-year-old girls and women | 6792 (3995) | 666.3 | 6795 (3982) | 830.0 | 0.80 | (0.77, 0.83)
Anti-HPV 16
9- through 15-year-old girls | 300 (276) | 6739.5 | 300 (270) | 6887.4 | 0.97 | (0.85, 1.11)
16- through 26-year-old girls and women | 6792 (4032) | 3131.1 | 6795 (4062) | 3156.6 | 0.99 | (0.96, 1.03)
Anti-HPV 18
9- through 15-year-old girls | 300 (276) | 1956.6 | 300 (269) | 1795.6 | 1.08 | (0.91, 1.29)
16- through 26-year-old girls and women | 6792 (4539) | 804.6 | 6795 (4541) | 678.7 | 1.19 | (1.14, 1.23)
CI=Confidence Interval
GMT=Geometric Mean Titer
cLIA=competitive Luminex Immunoassay

Study Supporting the Effectiveness of GARDASIL 9 against Vaccine HPV Types in 9- through 15-Year-Old Girls and Boys

Effectiveness of GARDASIL 9 against persistent infection and disease related to vaccine HPV types in 9- through 15-year-old girls and boys was inferred from non-inferiority comparison conducted in the PPI population in Study 2 of GMTs following vaccination with GARDASIL 9 among 9- through 15-year-old girls and boys with those among 16- through 26-year-old girls and women. Anti-HPV GMTs at Month 7 among 9- through 15-year-old girls and boys were non-inferior to anti-HPV GMTs among 16- through 26-year-old girls and women (Table 9).

Table 9: Comparison of Immune Responses (Based on cLIA) between the PPI [The PPI population consisted of individuals who received all three vaccinations within pre-defined day ranges, did not have major deviations from the study protocol, met predefined criteria for the interval between the Month 6 and Month 7 visit, were naïve (PCR negative [among 16- through 26-year old girls and women] and seronegative) to the relevant HPV type(s) prior to dose 1 and among 16- through 26-year-old girls and women remained PCR negative to the relevant HPV types through one month post-dose 3 (Month 7). The data are from Study 2 (NCT00943722).] Populations of 16- through 26-Year-Old Girls and Women, 9- through 15-Year-Old Girls, and 9- through 15-Year-Old Boys for All GARDASIL 9 Vaccine HPV Types (Study 2)
Population | N [N=Number of individuals randomized to the respective vaccination group who received at least one injection] | n [n=Number of individuals contributing to the analysis] | GMT mMU [mMU=milli-Merck Units] /mL | GMT Ratio relative to 16-through 26-year-old girls and women (95% CI) [Demonstration of non-inferiority required that the lower bound of the 95% CI of the GMT ratio be greater than 0.67]
Anti-HPV 6
9- through 15-year-old girls | 630 | 503 | 1703.1 | 1.89 (1.68, 2.12)
9- through 15-year-old boys | 641 | 537 | 2083.4 | 2.31 (2.06, 2.60)
16- through 26-year-old girls and women | 463 | 328 | 900.8 | 1
Anti-HPV 11
9- through 15-year-old girls | 630 | 503 | 1291.5 | 1.83 (1.63, 2.05)
9- through 15-year-old boys | 641 | 537 | 1486.3 | 2.10 (1.88, 2.36)
16- through 26-year-old girls and women | 463 | 332 | 706.6 | 1
Anti-HPV 16
9- through 15-year-old girls | 630 | 513 | 6933.9 | 1.97 (1.75, 2.21)
9- through 15-year-old boys | 641 | 546 | 8683.0 | 2.46 (2.20, 2.76)
16- through 26-year-old girls and women | 463 | 329 | 3522.6 | 1
Anti-HPV 18
9- through 15-year-old girls | 630 | 516 | 2148.3 | 2.43 (2.12, 2.79)
9- through 15-year-old boys | 641 | 544 | 2855.4 | 3.23 (2.83, 3.70)
16- through 26-year-old girls and women | 463 | 345 | 882.7 | 1
Anti-HPV 31
9- through 15-year-old girls | 630 | 506 | 1894.7 | 2.51 (2.21, 2.86)
9- through 15-year-old boys | 641 | 543 | 2255.3 | 2.99 (2.63, 3.40)
16- through 26-year-old girls and women | 463 | 340 | 753.9 | 1
Anti-HPV 33
9- through 15-year-old girls | 630 | 518 | 985.8 | 2.11 (1.88, 2.37)
9- through 15-year-old boys | 641 | 544 | 1207.4 | 2.59 (2.31, 2.90)
16- through 26-year-old girls and women | 463 | 354 | 466.8 | 1
Anti-HPV 45
9- through 15-year-old girls | 630 | 518 | 707.7 | 2.60 (2.25, 3.00)
9- through 15-year-old boys | 641 | 547 | 912.1 | 3.35 (2.90, 3.87)
16- through 26-year-old girls and women | 463 | 368 | 272.2 | 1
Anti-HPV 52
9- through 15-year-old girls | 630 | 517 | 962.2 | 2.21 (1.96, 2.49)
9- through 15-year-old boys | 641 | 545 | 1055.5 | 2.52 (2.22, 2.84)
16- through 26-year-old girls and women | 463 | 337 | 419.6 | 1
Anti-HPV 58
9- through 15-year-old girls | 630 | 516 | 1288.0 | 2.18 (1.94, 2.46)
9- through 15-year-old boys | 641 | 544 | 1593.3 | 2.70 (2.40, 3.03)
16- through 26-year-old girls and women | 463 | 332 | 590.5 | 1
cLIA=competitive Luminex Immunoassay
CI=Confidence Interval
GMT=Geometric Mean Titer

Study Supporting the Effectiveness of GARDASIL 9 against Vaccine HPV Types in 16- through 26-Year-Old Boys and Men

Effectiveness of GARDASIL 9 against persistent infection and disease related to vaccine HPV types in 16- through 26-year-old boys and men was inferred from non-inferiority comparison conducted in the PPI population in Study 7 of GMTs following vaccination with GARDASIL 9 among 16- through 26-year-old HM with those among 16- through 26-year-old girls and women. Anti-HPV GMTs at Month 7 among 16- through 26-year-old HM were non-inferior to anti-HPV GMTs among 16- through 26-year-old girls and women (Table 10). Study 7 also enrolled 313 16- through 26-year-old HIV-negative MSM. At Month 7, anti-HPV GMT ratios for MSM relative to HM ranged from 0.6 to 0.8, depending on HPV type. The GMT ratios for MSM relative to HM were generally similar to those previously observed in clinical trials with GARDASIL.

Table 10: Comparison of Immune Responses (Based on cLIA) between the PPI [The PPI population consisted of individuals who received all three vaccinations within pre-defined day ranges, did not have major deviations from the study protocol, met predefined criteria for the interval between the Month 6 and Month 7 visit, and were seronegative to the relevant HPV type(s) (types 6, 11, 16, 18, 31, 33, 45, 52, and 58) prior to dose 1. The data are from Study 7 (NCT01651949).] Populations of 16- through 26-Year-Old Girls and Women and 16- through 26-Year-Old Boys and Men Self-Identified as Heterosexual (HM) for All GARDASIL 9 Vaccine HPV Types (Study 7)
Population | N [Number of individuals randomized to the respective vaccination group who received at least one injection] | n [Number of individuals contributing to the analysis] | GMT mMU [mMU=milli-Merck Units] /mL | GMT Ratio relative to 16- through 26-year-old girls and women (95% CI) [Demonstration of non-inferiority required that the lower bound of the 95% CI of the GMT ratio be greater than 0.67]
Anti-HPV 6
16- through 26-year-old HM | 1103 | 847 | 782.0 | 1.11 (1.02, 1.21)
16- through 26-year-old girls and women | 1099 | 708 | 703.9 | 1
Anti-HPV 11
16- through 26-year-old HM | 1103 | 851 | 616.7 | 1.09 (1.00, 1.19)
16- through 26-year-old girls and women | 1099 | 712 | 564.9 | 1
Anti-HPV 16
16- through 26-year-old HM | 1103 | 899 | 3346.0 | 1.20 (1.10, 1.30)
16- through 26-year-old girls and women | 1099 | 781 | 2788.3 | 1
Anti-HPV 18
16- through 26-year-old HM | 1103 | 906 | 808.2 | 1.19 (1.08, 1.31)
16- through 26-year-old girls and women | 1099 | 831 | 679.8 | 1
Anti-HPV 31
16- through 26-year-old HM | 1103 | 908 | 708.5 | 1.24 (1.13, 1.37)
16- through 26-year-old girls and women | 1099 | 826 | 570.1 | 1
Anti-HPV 33
16- through 26-year-old HM | 1103 | 901 | 384.8 | 1.19 (1.10, 1.30)
16- through 26-year-old girls and women | 1099 | 853 | 322.0 | 1
Anti-HPV 45
16- through 26-year-old HM | 1103 | 909 | 235.6 | 1.27 (1.14, 1.41)
16- through 26-year-old girls and women | 1099 | 871 | 185.7 | 1
Anti-HPV 52
16- through 26-year-old HM | 1103 | 907 | 386.8 | 1.15 (1.05, 1.26)
16- through 26-year-old girls and women | 1099 | 849 | 335.2 | 1
Anti-HPV 58
16- through 26-year-old HM | 1103 | 897 | 509.8 | 1.25 (1.14, 1.36)
16- through 26-year-old girls and women | 1099 | 839 | 409.3 | 1
cLIA=competitive Luminex Immunoassay
CI=Confidence Interval
GMT=Geometric Mean Titer

Study Supporting the Effectiveness of GARDASIL 9 against Vaccine HPV Types in 27- through 45-Year-Old Women

Effectiveness of GARDASIL 9 against persistent infection and disease related to vaccine HPV types in 27- through 45-year-old women was supported by immunobridging comparisons conducted in the PPI population in Study 9. In Study 9, the GMT ratios of anti-HPV responses at Month 7 among 27- through 45-year-old women relative to anti-HPV responses among 16- through 26-year-old girls and women met the success criteria of having the lower bound of the 95% CI of the GMT ratios greater than 0.50 for HPV 16, 18, 31, 33, 45, 52, and 58 (Table 11).

Table 11: Comparison of Immune Responses (Based on cLIA) Between the PPI [The PPI population consisted of individuals who received all 3 vaccinations within pre-defined day ranges, did not have major deviations from the study protocol, met predefined criteria for the interval between the Month 6 and Month 7 visit, and were seronegative to the relevant HPV type(s) (types 16, 18, 31, 33, 45, 52, and 58) prior to dose 1. The data are from Study 9 (NCT03158220).] Populations of 27- through 45 Year-Old Women and 16- through 26-Year-Old Girls and Women for GARDASIL 9 Vaccine HPV Types (Study 9)
Population | N [Number of individuals randomized to the respective vaccination group who received at least 1 injection] | n [Number of individuals contributing to the analysis] | GMT mMU [mMU=milli-Merck Units] /mL | GMT Ratio relative to 16-through 26-year-old girls and women (95% CI) [Immunobridging required that the lower bound of the 95% CI of the GMT ratio be greater than 0.50]
Anti-HPV 6
27- through 45-year-old women | 640 | 448 | 638.4 | N.D [N.D=Not Determined. GMT ratios were not calculated because immunobridging comparison was not specified in the study protocol for HPV types 6 and 11.]
16- through 26-year-old girls and women | 570 | 421 | 787.8 | N.D
Anti-HPV 11
27- through 45-year-old women | 640 | 448 | 453.5 | N.D
16- through 26-year-old girls and women | 570 | 421 | 598.7 | N.D
Anti-HPV 16
27- through 45-year-old women | 640 | 448 | 2,147.5 | 0.70 (0.63, 0.77)
16- through 26-year-old girls and women | 570 | 436 | 3,075.8 | 1
Anti-HPV 18
27- through 45-year-old women | 640 | 471 | 532.1 | 0.71 (0.64, 0.80)
16- through 26-year-old girls and women | 570 | 421 | 744.5 | 1
Anti-HPV 31
27- through 45-year-old women | 640 | 488 | 395.7 | 0.66 (0.60, 0.74)
16- through 26-year-old girls and women | 570 | 447 | 596.1 | 1
Anti-HPV 33
27- through 45-year-old women | 640 | 493 | 259.0 | 0.73 (0.67, 0.80)
16- through 26-year-old girls and women | 570 | 457 | 354.5 | 1
Anti-HPV 45
27- through 45-year-old women | 640 | 515 | 145.6 | 0.68 (0.60, 0.76)
16- through 26-year-old girls and women | 570 | 470 | 214.9 | 1
Anti-HPV 52
27- through 45-year-old women | 640 | 496 | 244.7 | 0.71 (0.64, 0.78)
16- through 26-year-old girls and women | 570 | 456 | 346.5 | 1
Anti-HPV 58
27- through 45-year-old women | 640 | 478 | 296.4 | 0.69 (0.63, 0.76)
16- through 26-year-old girls and women | 570 | 451 | 428.0 | 1
cLIA=Competitive Luminex Immunoassay
CI=Confidence Interval
GMT=Geometric Mean Titers

Immune Response to GARDASIL 9 across All Clinical Trials

Across all clinical trials, at least 99.2% of individuals included in the analyses for each of the nine vaccine HPV types became seropositive by Month 7. Anti-HPV GMTs at Month 7 among 9- through 15-year-old girls and boys and 16- through 26-year-old boys and men were comparable to anti-HPV responses among 16- through 26-year-old girls and women in the combined database of immunogenicity studies for GARDASIL 9.

Persistence of Immune Response to GARDASIL 9

In an extension study of individuals in Study 2, among girls and boys 9 through 15 years of age at enrollment (range of 494 to 525 subjects with evaluable data across HPV types) and followed for 10 years post dose 3, anti-HPV 6, 11, 16, 18, 31, 33, 45, 52 and 58 GMTs as measured by cLIA were decreased compared with corresponding values at one-month post-dose 3. The proportion of seropositive subjects ranged from 99.6% to 100% at one month post-dose 3 and from 81.3% to 97.7% at 10 years post-dose 3, depending on HPV type.

Administration of GARDASIL 9 to Individuals Previously Vaccinated with GARDASIL

Study 4 evaluated the immunogenicity of 3 doses of GARDASIL 9 in 921 girls and women (12 through 26 years of age) who had previously been vaccinated with 3 doses of GARDASIL. Prior to enrollment in the study, over 99% of subjects had received three injections of GARDASIL within a one year period. The time interval between the last injection of GARDASIL and the first injection of GARDASIL 9 ranged from approximately 12 to 36 months.

Seropositivity to HPV Types 6, 11, 16, 18, 31, 33, 45, 52, and 58 in the per protocol population ranged from 98.3 to 100% by Month 7 in individuals who received GARDASIL 9. The anti-HPV 31, 33, 45, 52 and 58 GMTs for the population previously vaccinated with GARDASIL were 25-63% of the GMTs in the combined populations from Studies 1, 2, 3, and 5, who had not previously received GARDASIL, although the clinical relevance of these differences is unknown. Efficacy of GARDASIL 9 in preventing infection and disease related to HPV Types 31, 33, 45, 52, and 58 in individuals previously vaccinated with GARDASIL has not been assessed.

Concomitant Use of Hormonal Contraceptives

Among 7,269 female recipients of GARDASIL 9 (16 through 26 years of age), 60.2% used hormonal contraceptives during the vaccination period of clinical studies 1 and 2. Use of hormonal contraceptives did not appear to affect the type of specific immune responses to GARDASIL 9.

14.7 Immune Responses to GARDASIL 9 Using a 2-Dose Regimen in Individuals 9 through 14 Years of Age

Effectiveness of GARDASIL 9 against persistent infection and disease related to vaccine HPV types in 9- through 14-year-old girls and boys who received a 2-dose regimen was inferred from non-inferiority comparison conducted in the PPI population in Study 8 of GMTs following vaccination with GARDASIL 9 among 9- through 14-year-old girls and boys who received a 2-dose regimen (at 0, 6 months or 0, 12 months) with those among 16- through 26-year-old girls and women who received a 3-dose regimen (at 0, 2, 6 months). Anti-HPV GMTs at one month after the last dose among 9- through 14-year-old girls and boys who received 2 doses of GARDASIL 9 were non-inferior to anti-HPV GMTs among 16- through 26-year-old girls and women who received 3 doses of GARDASIL 9 (Table 12).

One month following the last dose of the assigned regimen, between 97.9% and 100% of subjects across all groups became seropositive for antibodies against the 9 vaccine HPV types (Table 12).

In the same study, in girls and boys 9 through 14 years old, GMTs at one month after the last vaccine dose were numerically lower for some vaccine types after a 2-dose schedule than in girls 9 through 14 years old after a 3-dose schedule (HPV types 18, 31, 45, and 52 after 0, 6 months and HPV type 45 after 0, 12 months; Table 12). The clinical relevance of these findings is unknown.

Duration of immunity of a 2-dose schedule of GARDASIL 9 has not been established.

Table 12: Summary of Anti-HPV cLIA Geometric Mean Titers in the PPI [The PPI population consisted of individuals who received all assigned vaccinations within pre-defined day ranges, did not have major deviations from the study protocol, met predefined criteria for the interval between the last vaccination dose and blood collection for immunogenicity assessment, and were seronegative to the relevant HPV type(s) (types 6, 11, 16, 18, 31, 33, 45, 52, and 58) prior to dose 1.] Population at One Month After the Last Vaccine Dose Among Subjects Who Received 2 Doses [2-dose regimen (0, 6): vaccination at Day 1 and Month 6; 2-dose regimen (0, 12): vaccination at Day 1 and Month 12; 3-dose regimen (0, 2, 6): vaccination at Day 1, Month 2, and Month 6. The data are from Study 8 (NCT01984697).] or 3 Doses of GARDASIL 9 (Study 8)
Population (Regimen) | N | n | GMT mMU [mMU=milli-Merck Units] /mL | GMT Ratio relative to 3-dose regimen in 16- through 26-year-old girls and women (95% CI)
Anti-HPV 6
9- to 14-year-old girls (0, 6) | 301 | 258 | 1657.9 | 2.15 (1.83, 2.53) [Demonstration of non-inferiority required that the lower bound of the 95% CI of the GMT ratio be greater than 0.67]
9- to 14-year-old boys (0, 6) | 301 | 263 | 1557.4 | 2.02 (1.73, 2.36)
9- to 14-year-old girls and boys (0, 12) | 300 | 257 | 2678.8 | 3.47 (2.93, 4.11)
9- to 14-year-old girls (0, 2, 6) | 300 | 254 | 1496.1 | 1.94 (1.65, 2.29) [Exploratory analysis; criterion for non-inferiority was not pre-specified]
16- to 26-year-old women (0, 2, 6) | 314 | 238 | 770.9 | 1
Anti-HPV 11
9- to 14-year-old girls (0, 6) | 301 | 258 | 1388.9 | 2.39 (2.03, 2.82)
9- to 14-year-old boys (0, 6) | 301 | 264 | 1423.9 | 2.45 (2.09, 2.88)
9- to 14-year-old girls and boys (0, 12) | 300 | 257 | 2941.8 | 5.07 (4.32, 5.94)
9- to 14-year-old girls (0, 2, 6) | 300 | 254 | 1306.3 | 2.25 (1.90, 2.66)
16- to 26-year-old women (0, 2, 6) | 314 | 238 | 580.5 | 1
Anti-HPV 16
9- to 14-year-old girls (0, 6) | 301 | 272 | 8004.9 | 2.54 (2.14, 3.00)
9- to 14-year-old boys (0, 6) | 301 | 273 | 8474.8 | 2.69 (2.29, 3.15)
9- to 14-year-old girls and boys (0, 12) | 300 | 264 | 14329.3 | 4.54 (3.84, 5.37)
9- to 14-year-old girls (0, 2, 6) | 300 | 269 | 6996.0 | 2.22 (1.89, 2.61)
16- to 26-year-old women (0, 2, 6) | 314 | 249 | 3154.0 | 1
Anti-HPV 18
9- to 14-year-old girls (0, 6) | 301 | 272 | 1872.8 | 2.46 (2.05, 2.96)
9- to 14-year-old boys (0, 6) | 301 | 272 | 1860.9 | 2.44 (2.04, 2.92)
9- to 14-year-old girls and boys (0, 12) | 300 | 266 | 2810.4 | 3.69 (3.06, 4.45)
9- to 14-year-old girls (0, 2, 6) | 300 | 270 | 2049.3 | 2.69 (2.24, 3.24)
16- to 26-year-old women (0, 2, 6) | 314 | 267 | 761.5 | 1
Anti-HPV 31
9- to 14-year-old girls (0, 6) | 301 | 272 | 1436.3 | 2.51 (2.10, 3.00)
9- to 14-year-old boys (0, 6) | 301 | 271 | 1498.2 | 2.62 (2.20, 3.12)
9- to 14-year-old girls and boys (0, 12) | 300 | 268 | 2117.5 | 3.70 (3.08, 4.45)
9- to 14-year-old girls (0, 2, 6) | 300 | 271 | 1748.3 | 3.06 (2.54, 3.67)
16- to 26-year-old women (0, 2, 6) | 314 | 264 | 572.1 | 1
Anti-HPV 33
9- to 14-year-old girls (0, 6) | 301 | 273 | 1030.0 | 2.96 (2.50, 3.50)
9- to 14-year-old boys (0, 6) | 301 | 271 | 1040.0 | 2.99 (2.55, 3.50)
9- to 14-year-old girls and boys (0, 12) | 300 | 269 | 2197.5 | 6.31 (5.36, 7.43)
9- to 14-year-old girls (0, 2, 6) | 300 | 275 | 796.4 | 2.29 (1.95, 2.68)
16- to 26-year-old women (0, 2, 6) | 314 | 279 | 348.1 | 1
Anti-HPV 45
9- to 14-year-old girls (0, 6) | 301 | 274 | 357.6 | 1.67 (1.38, 2.03)
9- to 14-year-old boys (0, 6) | 301 | 273 | 352.3 | 1.65 (1.37, 1.99)
9- to 14-year-old girls and boys (0, 12) | 300 | 268 | 417.7 | 1.96 (1.61, 2.37)
9- to 14-year-old girls (0, 2, 6) | 300 | 275 | 661.7 | 3.10 (2.54, 3.77)
16- to 26-year-old women (0, 2, 6) | 314 | 280 | 213.6 | 1
Anti-HPV 52
9- to 14-year-old girls (0, 6) | 301 | 272 | 581.1 | 1.60 (1.36, 1.87)
9- to 14-year-old boys (0, 6) | 301 | 273 | 640.4 | 1.76 (1.51, 2.05)
9- to 14-year-old girls and boys (0, 12) | 300 | 268 | 1123.4 | 3.08 (2.64, 3.61)
9- to 14-year-old girls (0, 2, 6) | 300 | 275 | 909.9 | 2.50 (2.12, 2.95)
16- to 26-year-old women (0, 2, 6) | 314 | 271 | 364.2 | 1
Anti-HPV 58
9- to 14-year-old girls (0, 6) | 301 | 270 | 1251.2 | 2.55 (2.15, 3.01)
9- to 14-year-old boys (0, 6) | 301 | 270 | 1325.7 | 2.70 (2.30, 3.16)
9- to 14-year-old girls and boys (0, 12) | 300 | 265 | 2444.6 | 4.98 (4.23, 5.86)
9- to 14-year-old girls (0, 2, 6) | 300 | 273 | 1229.3 | 2.50 (2.11, 2.97)
16- to 26-year-old women (0, 2, 6) | 314 | 261 | 491.1 | 1
N = Number of individuals randomized to the respective vaccination group who received at least 1 injection
n = Number of individuals contributing to the analysis
CI=Confidence Interval
cLIA=competitive Luminex Immunoassay
GMT=Geometric Mean Titer

14.8 Studies with Menactra and Adacel

In Study 5, the safety and immunogenicity of co-administration of GARDASIL 9 with Menactra [Meningococcal (Groups A, C, Y and W-135) Polysaccharide Diphtheria Toxoid Conjugate Vaccine] and Adacel [Tetanus Toxoid, Reduced Diphtheria Toxoid and Acellular Pertussis Vaccine Adsorbed (Tdap)] (same visit, injections at separate sites) were evaluated in 1,237 boys and girls 11 through 15 years of age at enrollment.

One group received GARDASIL 9 in one limb and both Menactra and Adacel, as separate injections, in the opposite limb concomitantly on Day 1 (n = 619). The second group received the first dose of GARDASIL 9 on Day 1 in one limb then Menactra and Adacel, as separate injections, at Month 1 in the opposite limb (n = 618). Subjects in both vaccination groups received the second dose of GARDASIL 9 at Month 2 and the third dose at Month 6. Immunogenicity was assessed for all vaccines one month post vaccination (one dose for Menactra and Adacel and three doses for GARDASIL 9).

Assessments of post-vaccination immune responses included type-specific antibody GMTs for each of the vaccine HPV types at four weeks following the last dose of GARDASIL 9; GMTs for anti-filamentous hemagglutinin, anti-pertactin, and anti-fimbrial antibodies at four weeks following Adacel; percentage of subjects with anti-tetanus toxin and anti-diphtheria toxin antibody concentrations ≥0.1 IU/mL at four weeks following Adacel; and percentage of subjects with ≥4-fold rise from pre-vaccination baseline in antibody titers against N. meningitidis serogroups A, C, Y, and W-135 at four weeks following Menactra. Based on these measures, concomitant administration of GARDASIL 9 with Menactra and Adacel did not interfere with the antibody responses to any of the vaccines when compared with non-concomitant administration of GARDASIL 9 with Menactra and Adacel.

15 REFERENCES

1. Study 1 NCT00543543
2. Study 2 NCT00943722
3. Study 3 NCT01304498
4. Study 4 NCT01047345
5. Study 5 NCT00988884
6. Study 6 NCT01073293
7. Study 7 NCT01651949
8. Study 8 NCT01984697
9. Study A NCT01432574
10. Study B NCT00090285
11. Study 9 NCT03158220

16 HOW SUPPLIED/STORAGE AND HANDLING

GARDASIL 9 is supplied in vials and syringes.

Carton of ten 0.5-mL single-dose vials. NDC 0006-4119-03

Carton of ten 0.5-mL single-dose prefilled Luer Lock syringes with tip caps. NDC 0006-4121-02

STORAGE AND HANDLING

Store refrigerated at 2 to 8°C (36 to 46°F). Do not freeze. Protect from light.

GARDASIL 9 should be administered as soon as possible after being removed from refrigeration. GARDASIL 9 can be administered provided total (cumulative multiple excursion) time out of refrigeration (at temperatures between 8°C and 25°C) does not exceed 72 hours. Cumulative multiple excursions between 0°C and 2°C are also permitted as long as the total time between 0°C and 2°C does not exceed 72 hours. These are not, however, recommendations for storage.

17 PATIENT COUNSELING INFORMATION

Advise the patient to read the FDA-approved patient labeling (Patient Information).

Inform the patient, parent, or guardian:

- Vaccination does not eliminate the necessity for women to continue to undergo recommended cervical cancer screening. Women who receive GARDASIL 9 should continue to undergo cervical cancer screening per standard of care.
- Recipients of GARDASIL 9 should not discontinue anal cancer screening if it has been recommended by a health care provider.
- GARDASIL 9 has not been demonstrated to provide protection against disease from vaccine and non-vaccine HPV types to which a person has previously been exposed through sexual activity.
- Since syncope has been reported following HPV vaccination sometimes resulting in falling with injury, observation for 15 minutes after administration is recommended.
- Vaccine information is required to be given with each vaccination to the patient, parent, or guardian.
- Provide information regarding benefits and risks associated with vaccination.
- Safety and effectiveness of GARDASIL 9 have not been established in pregnant women.
- It is important to complete the full vaccination series unless contraindicated.
- Report any adverse reactions to their health care provider.

Manuf. and Dist. by: Merck Sharp & Dohme LLC
Rahway, NJ 07065, USA

For patent information: www.msd.com/research/patent

The trademarks depicted herein are owned by their respective companies.

Copyright © 2006-2025 Merck & Co., Inc., Rahway, NJ, USA, and its affiliates.
All rights reserved.

uspi-v503-i-2503r017

Patient Information about GARDASIL®9 (pronounced "gard-Ah-sill nīn") (Human Papillomavirus 9-valent Vaccine, Recombinant)

Read this information with care before getting GARDASIL®9. You or your child (the person getting GARDASIL 9) will need 2 or 3 doses of the vaccine, depending on how old you are. It is important to read this information before getting each dose. This information does not take the place of talking with your health care professional about GARDASIL 9.

What is GARDASIL 9?

GARDASIL 9 is a vaccine given to individuals 9 through 45 years of age to help protect against diseases caused by some types of Human Papillomavirus (HPV).

What diseases can GARDASIL 9 help protect against?

In girls and women 9 through 45 years of age, GARDASIL 9 helps protect against:

- Cervical cancer
- Vulvar and vaginal cancers
- Anal cancer
- Certain head and neck cancers, such as throat and back of mouth cancers
- Precancerous cervical, vulvar, vaginal and anal lesions
- Genital warts

In boys and men 9 through 45 years of age, GARDASIL 9 helps protect against:

- Anal cancer
- Certain head and neck cancers, such as throat and back of mouth cancers
- Precancerous anal lesions
- Genital warts

These diseases may have many causes, including HPV Types 6, 11, 16, 18, 31, 33, 45, 52, and 58. GARDASIL 9 only protects against diseases caused by these nine types of HPV.

People cannot get HPV or any of these diseases from GARDASIL 9.

What important information about GARDASIL 9 should I know?

GARDASIL 9:

- Does not remove the need for screening for cervical, vulvar, vaginal, anal, and certain head and neck cancers, such as throat and back of mouth cancers as recommended by a health care professional; women should still get routine cervical cancer screening.
- Does not protect the person getting GARDASIL 9 from a disease that is caused by other types of HPV, other viruses or bacteria.
- Does not treat HPV infection.
- Does not protect the person getting GARDASIL 9 from HPV types that he/she may already have.

GARDASIL 9 may not fully protect each person who gets it.

Who should not get GARDASIL 9?

Anyone with an allergic reaction to:

- A previous dose of GARDASIL 9
- A previous dose of GARDASIL®
- Yeast (severe allergic reaction)
- Amorphous aluminum hydroxyphosphate sulfate
- Polysorbate 80

What should I tell the health care professional before getting GARDASIL 9?

Tell the health care professional if you or your child (the person getting GARDASIL 9):

- Are pregnant or planning to get pregnant.
- Have immune problems, like HIV or cancer.
- Take medicines that affect the immune system.
- Have a fever over 100°F (37.8°C).
- Might have had an allergic reaction to a previous dose of GARDASIL 9 or GARDASIL.
- Take any medicines, even those you can buy over the counter.

The health care professional will help decide if you or your child should get the vaccine.

How is GARDASIL 9 given?

GARDASIL 9 is an injection that is usually given in the arm muscle. GARDASIL 9 may be given as 2 or 3 injections.

For persons who are | You will need | Given as
9 through 14 years old | 2 injections [If the second injection is given earlier than 5 months after the first injection, you will need to get a third injection at least 4 months after the second injection was given.] | Dose 1: first injection Dose 2: second injection given between 6 and 12 months after the first injection
9 through 14 years old | or 3 injections [The need to use a 3-dose schedule instead of a 2-dose schedule will be determined by your health care professional.] | Dose 1: first injection Dose 2: second injection given 2 months after the first injection Dose 3: third injection given 6 months after the first injection
15 through 45 years old | 3 injections | Dose 1: first injection Dose 2: second injection given 2 months after the first injection Dose 3: third injection given 6 months after the first injection

Make sure that you or your child gets all doses recommended by your health care professional so that you or your child gets the best protection. If the person getting GARDASIL 9 misses a dose, tell the health care professional and they will decide when to give the missed dose. It is important that you follow the instructions of your health care professional regarding return visits for the follow-up doses.

Fainting can happen after getting an HPV vaccine. Sometimes people who faint can fall and hurt themselves. For this reason, the health care professional may ask the person getting GARDASIL 9 to sit or lie down for 15 minutes after getting the vaccine. Some people who faint might shake or become stiff. The health care professional may need to treat the person getting GARDASIL 9.

Can I get GARDASIL 9 if I have already gotten GARDASIL?

If you have already gotten GARDASIL, talk to your health care professional to see if GARDASIL 9 is right for you.

Can I get GARDASIL 9 with other vaccines?

GARDASIL 9 can be given at the same time as:

- Menactra [Meningococcal (Groups A, C, Y and W-135) Polysaccharide Diphtheria Toxoid Conjugate Vaccine]
- Adacel [Tetanus Toxoid, Reduced Diphtheria Toxoid and Acellular Pertussis Vaccine Adsorbed (Tdap)]

What are the possible side effects of GARDASIL 9?

The most common side effects seen with GARDASIL 9 are:

- pain, swelling, redness, itching, bruising, bleeding, and a lump where you got the injection
- headache
- fever
- nausea
- dizziness
- tiredness
- diarrhea
- abdominal pain
- sore throat

Studies show that there was more swelling where the injection was given when GARDASIL 9 was given at the same time as Menactra and/or Adacel.

Tell the health care professional if you have any of these problems because these may be signs of an allergic reaction:

- difficulty breathing
- wheezing (bronchospasm)
- hives
- rash

Additional side effects that have been reported during general use for GARDASIL 9 are shown below. Side effects reported during the general use of GARDASIL are also shown below. GARDASIL side effects are reported as they may be relevant to GARDASIL 9 since the vaccines are similar in composition.

GARDASIL 9

- vomiting
- hives
- lump where you got the injection

The following side effects have been seen with the general use of GARDASIL.

GARDASIL

- swollen glands (neck, armpit, or groin)
- joint pain
- unusual tiredness, weakness, or confusion
- chills
- generally feeling unwell
- leg pain
- shortness of breath
- chest pain
- aching muscles
- muscle weakness
- seizure
- bad stomachache
- bleeding or bruising more easily than normal
- skin infection
- lump where you got the injection

You should contact your health care professional right away if you get any symptoms that bother you.

For a more complete list of side effects, ask the health care professional.

Call your health care professional for medical advice about side effects. You may also report any side effects to your doctor or directly to Vaccine Adverse Event Reporting System (VAERS). The VAERS toll-free number is 1-800-822-7967 or report online to www.vaers.hhs.gov .

GARDASIL 9 was not studied in women who knew they were pregnant. Tell the doctor or health care professional if you or your child (the person getting GARDASIL 9), is pregnant or is planning to get pregnant.

What is in GARDASIL 9?

GARDASIL 9 contains:

- Proteins of HPV Types 6, 11, 16, 18, 31, 33, 45, 52, and 58
- Amorphous aluminum hydroxyphosphate sulfate
- Yeast protein
- Sodium chloride
- L-histidine
- Polysorbate 80
- Sodium borate
- Water

This document is a summary of information about GARDASIL 9.

To learn more about GARDASIL 9, please talk to the health care professional or visit www.GARDASIL9.com .

Manuf. and Dist. by: Merck Sharp & Dohme LLC
Rahway, NJ 07065, USA

For patent information: www.msd.com/research/patent

The trademarks depicted herein are owned by their respective companies.

Copyright © 2006-2025 Merck & Co., Inc., Rahway, NJ, USA, and its affiliates.
All rights reserved.

Revised: 03/2025

usppi-v503-i-2503r008

PRINCIPAL DISPLAY PANEL - 0.5 mL Vial Carton

NDC 0006-4119-03

10 Single-dose 0.5-mL Vials

REFRIGERATE

Human Papillomavirus 9-valent Vaccine, Recombinant

GARDASIL® 9

Suspension for intramuscular injection

Each 0.5-mL dose contains human papillomavirus L1 protein of each type adsorbed on amorphous aluminum
hydroxyphosphate sulfate adjuvant as follows:
Type 6 (30 mcg), Type 11 (40 mcg), Type 16 (60 mcg), Type 18 (40 mcg), Type 31 (20 mcg), Type 33 (20 mcg),
Type 45 (20 mcg), Type 52 (20 mcg), Type 58 (20 mcg).

Vaccine is prepared from fermentation cultures of a recombinant strain of yeast Saccharomyces cerevisiae
containing the genes for the human papillomavirus L1 protein of each type (6, 11, 16, 18, 31, 33, 45, 52, 58).

Contains no preservative or antibiotics.

Rx only

PRINCIPAL DISPLAY PANEL - 0.5 mL Syringe Carton

NDC 0006-4121-02

10 Single-dose 0.5-mL Syringes

REFRIGERATE

Human Papillomavirus
9-valent Vaccine, Recombinant

GARDASIL® 9

Suspension for intramuscular injection

Each 0.5-mL dose contains human papillomavirus L1 protein of each type
adsorbed on amorphous aluminum hydroxyphosphate sulfate adjuvant
as follows:
Type 6 (30 mcg), Type 11 (40 mcg), Type 16 (60 mcg), Type 18 (40 mcg),
Type 31 (20 mcg), Type 33 (20 mcg), Type 45 (20 mcg), Type 52 (20 mcg),
Type 58 (20 mcg).

Vaccine is prepared from fermentation cultures of a recombinant strain of yeast
Saccharomyces cerevisiae containing the genes for the human papillomavirus
L1 protein of each type (6, 11, 16, 18, 31, 33, 45, 52, 58).

Contains no preservative or antibiotics.

Rx only